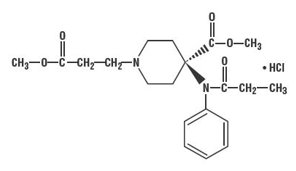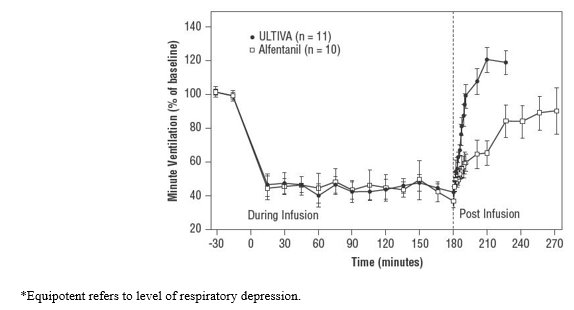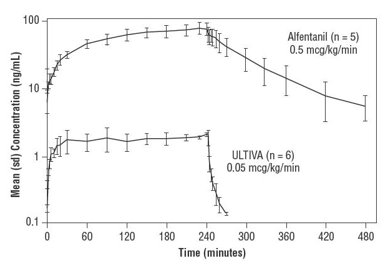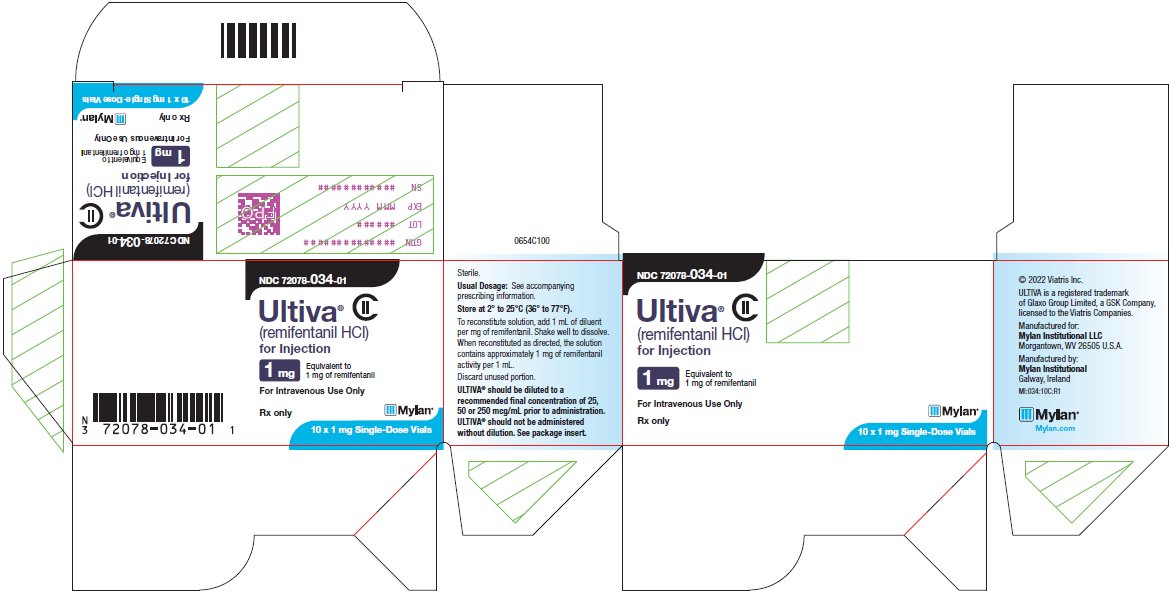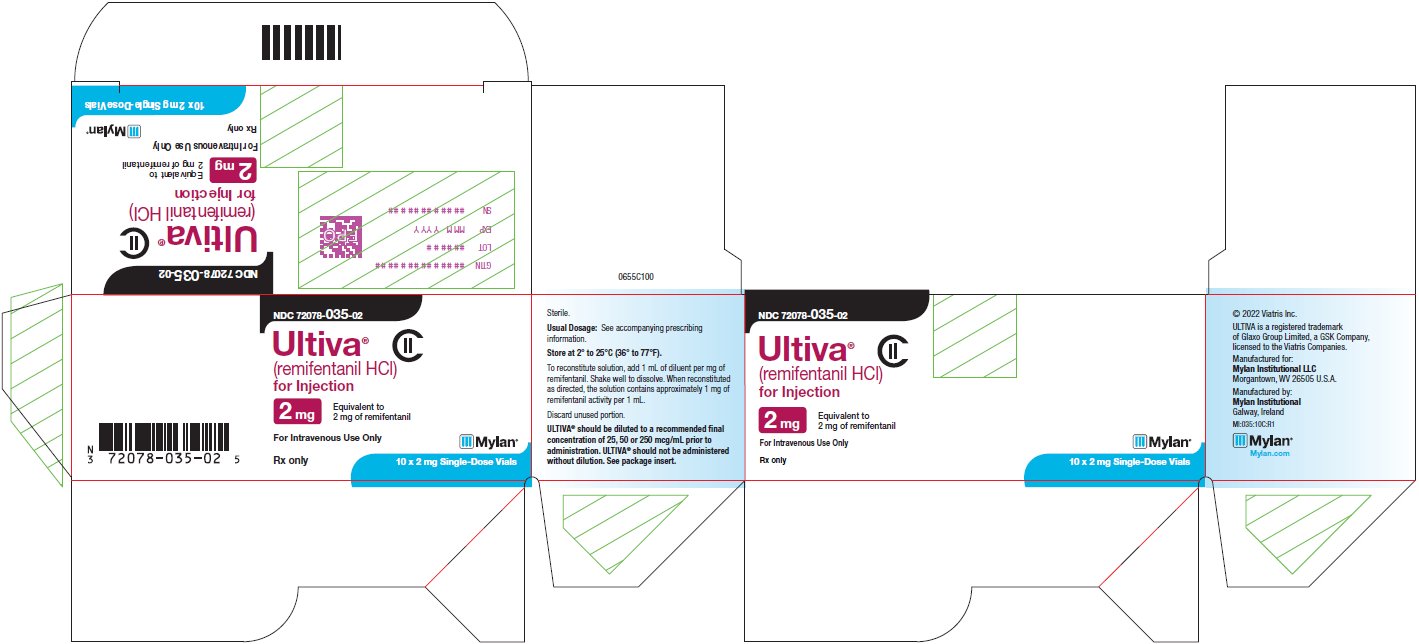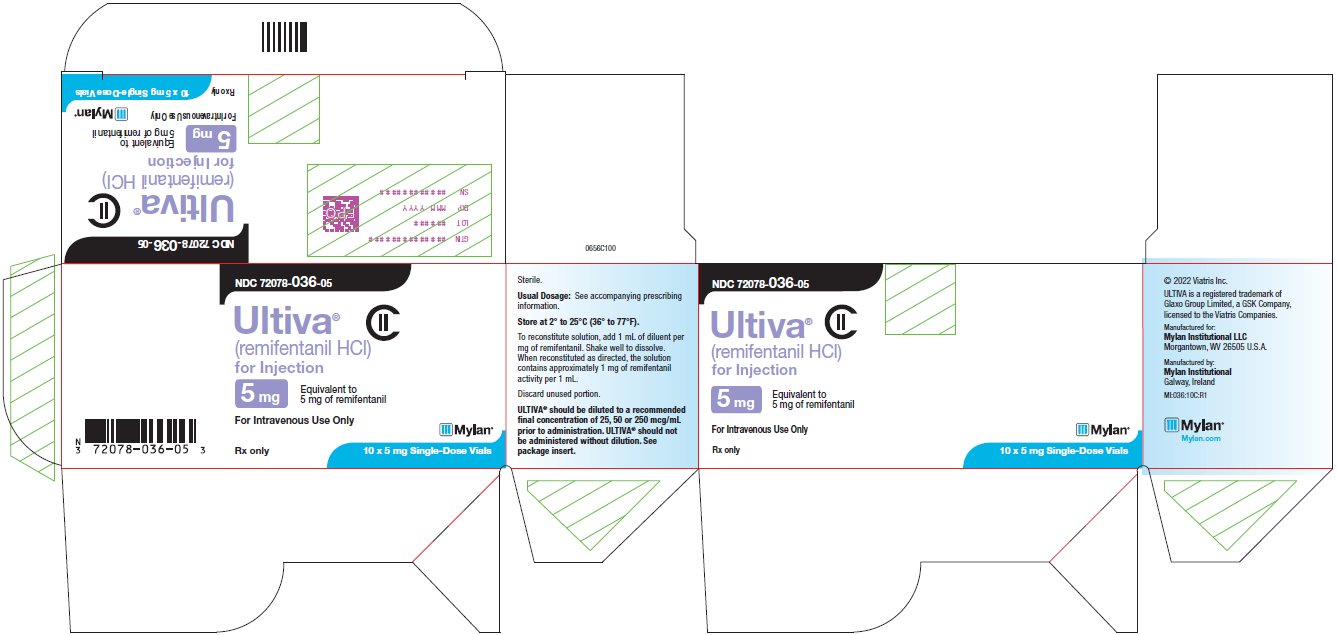 DRUG LABEL: Ultiva
NDC: 72078-034 | Form: INJECTION, POWDER, LYOPHILIZED, FOR SOLUTION
Manufacturer: Mylan Institutional LLC
Category: prescription | Type: HUMAN PRESCRIPTION DRUG LABEL
Date: 20251208
DEA Schedule: CII

ACTIVE INGREDIENTS: Remifentanil Hydrochloride 1 mg/1 mL
INACTIVE INGREDIENTS: Glycine 15 ug/1 mL; Hydrochloric Acid

HIGHLIGHTS OF PRESCRIBING INFORMATION

These highlights do not include all the information needed to use ULTIVA safely and effectively. See full prescribing information for ULTIVA.
ULTIVA® (remifentanil hydrochloride), for injection, for intravenous use, CII
Initial U.S. Approval: 1996

RECENT MAJOR CHANGES

Dosage and Administration (2.1, 2.5) 12/2025
Warnings and Precautions (5.2, 5.3) 12/2025

WARNING: SERIOUS AND LIFE-THREATENING RISKS FROM USE OF ULTIVA

See full prescribing information for complete boxed warning.

- ULTIVA exposes users to the risks of addiction, abuse, and misuse. Assess patient’s risk before prescribing and reassess regularly for the development of these behaviors and conditions.(5.1)
- Serious, life-threatening, or fatal respiratory depression may occur with use of ULTIVA, especially during initiation or following a dosage increase. To reduce the risk of respiratory depression, proper dosing and titration of ULTIVA are essential. (5.2)
- Concomitant use of opioids with benzodiazepines or other central nervous system (CNS) depressants, including alcohol, may result in profound sedation, respiratory depression, coma, and death. Reserve concomitant prescribing for use in patients for whom alternative treatment options are inadequate. (5.3, 7)

1 INDICATIONS AND USAGE

ULTIVA is an opioid agonist indicated for intravenous administration:

- As an analgesic agent for use during the induction and maintenance of general anesthesia for inpatient and outpatient procedures. (1)
- For continuation as an analgesic into the immediate postoperative period in adult patients under the direct supervision of an anesthesia practitioner in a postoperative anesthesia care unit or intensive care setting. (1)
- As an analgesic component of monitored anesthesia care in adult patients. (1)

2 DOSAGE AND ADMINISTRATION

- Monitor patients closely for respiratory depression when initiating therapy and following dosage increases and adjust the dosage accordingly. (2.1)
- Administration: Continuous infusions of ULTIVA should be administered only by an infusion device. (2.1)
- Initial Dosage in Adults: See full prescribing information for recommended doses in adult patients. (2.2, 2.3)
- Initial Dosage in Pediatric Patients: See full prescribing information for recommended doses in pediatric patients. (2.2)
- Geriatric Patients: The starting doses should be decreased by 50% in elderly patients (> 65 years). (2.6)

3 DOSAGE FORMS AND STRENGTHS

For injection: 1 mg, 2 mg, and 5 mg for intravenous administration after reconstitution and dilution (3)

4 CONTRAINDICATIONS

ULTIVA is contraindicated:

- For epidural or intrathecal administration due to the presence of glycine in the formulation. (4)
- In patients with hypersensitivity to remifentanil (e.g., anaphylaxis). (4)

5 WARNINGS AND PRECAUTIONS

- Life-Threatening Respiratory Depression: Monitor closely, particularly during initiation and titration. (5.2)
- Risks from Use as Postoperative Analgesia with Concomitant Benzodiazepines or other CNS Depressants: Hypotension, profound sedation, respiratory depression, coma, and death may result from the concomitant use of ULTIVA with benzodiazepines or other CNS depressants (5.3)
- Opioid-Induced Hyperalgesia and Allodynia: Opioid-Induced Hyperalgesia (OIH) occurs when an opioid analgesic paradoxically causes an increase in pain, or an increase in sensitivity to pain. If OIH is suspected, carefully consider appropriately decreasing the dose of the current opioid analgesic or opioid rotation. (5.4)
- Serotonin Syndrome: Potentially life-threatening condition could result from concomitant serotonergic drug administration. Discontinue ULTIVA if serotonin syndrome is suspected. (5.5)
- Skeletal Muscle Rigidity: is related to the dose and speed of administration. Muscle rigidity induced by ULTIVA should be managed in the context of the patient's clinical condition. (5.6)
- Potential Inactivation by Nonspecific Esterases in Blood Products: ULTIVA should not be administered into the same IV tubing with blood due to potential inactivation by nonspecific esterases in blood products. (5.7)
- Bradycardia: Monitor heart rate during dosage initiation and titration. It is responsive to ephedrine or anticholinergic drugs (5.8)
- Hypotension: Monitor blood pressure during dosage initiation and titration. It is responsive to decreases in the administration of ULTIVA or to IV fluids or catecholamine administration (5.9)
- Intraoperative Awareness: Inoperative awareness has been reported in patients under 55 years of age when ULTIVA has been administered with propofol infusion rates of ≤ 75 mcg/kg/min (5.10)
- Risks of Use in Spontaneously Breathing Patients with Increased Intracranial Pressure, Brain Tumors, Head Injury, or Impaired Consciousness: Monitor for sedation and respiratory depression. (5.11)
- Risks of Use in Patients with Biliary Tract Disease: Monitor patients with biliary tract disease, including acute pancreatitis, for worsening symptoms. (5.12)
- Increased Risk of Seizures in Patients with Seizure Disorders: Monitor patients with a history of seizure disorders for worsened seizure control during ULTIVA therapy. (5.13)
- Rapid Offset of Action: Standard monitoring should be maintained in the postoperative period to ensure adequate recovery without stimulation. (5.14)

6 ADVERSE REACTIONS

Most common adverse reactions (incidence ≥ 1%) were respiratory depression, bradycardia, hypotension, and skeletal muscle rigidity. (6)

To report SUSPECTED ADVERSE REACTIONS, contact Mylan at 1-877-446-3679 (1-877-4-INFO-RX) or FDA at 1-800-FDA-1088 or www.fda.gov/medwatch.

7 DRUG INTERACTIONS

- Mixed Agonist/Antagonist and Partial Agonist Opioid Analgesics: May reduce the analgesic effect of ULTIVA and/or precipitate withdrawal symptoms. If concomitant use is warranted, carefully observe the patient, particularly during treatment initiation and dose adjustment. (7)

8 USE IN SPECIFIC POPULATIONS

- Pregnancy: May cause fetal harm. (8.1)
- Labor or Delivery: Respiratory depression and other opioid effects may occur in newborns whose mothers are given ULTIVA shortly before delivery. (8.1)
- Lactation: Infants exposed to ULTIVA through breast milk should be monitored for excess sedation and respiratory depression. (8.2)
- Pediatric Use: ULTIVA has not been studied in pediatric patients for use as a postoperative analgesic or as an analgesic component of monitored anesthesia care. (8.4)

FULL PRESCRIBING INFORMATION

WARNING: SERIOUS AND LIFE-THREATENING RISKS FROM USE OF ULTIVA

Addiction, Abuse, and Misuse

Because the use of ULTIVA exposes patients and other users to the risks of opioid addiction, abuse, and misuse, which can lead to overdose and death, assess each patient’s risk prior to prescribing and reassess all patients regularly for the development of these behaviors and conditions [see Warnings and Precautions (5.1)].

Life-Threatening Respiratory Depression

Serious, life-threatening, or fatal respiratory depression may occur with use of ULTIVA, especially during initiation or following a dosage increase. To reduce the risk of respiratory depression, proper dosing and titration of ULTIVA are essential [see Warnings and Precautions (5.2)].

Risks From Concomitant Use With Benzodiazepines Or Other CNS Depressants

Concomitant use of opioids with benzodiazepines or other central nervous system (CNS) depressants, including alcohol, may result in profound sedation, respiratory depression, coma, and death. Reserve concomitant prescribing of ULTIVA and benzodiazepines or other CNS depressants for use in patients for whom alternative treatment options are inadequate [see Warnings and Precautions (5.3), Drug Interactions (7)].

1 INDICATIONS AND USAGE

ULTIVA is indicated for intravenous (IV) administration:

- As an analgesic agent for use during the induction and maintenance of general anesthesia for inpatient and outpatient procedures.
- For continuation as an analgesic into the immediate postoperative period in adult patients under the direct supervision of an anesthesia practitioner in a postoperative anesthesia care unit or intensive care setting.
- As an analgesic component of monitored anesthesia care in adult patients.

2 DOSAGE AND ADMINISTRATION

2.1 Important Dosage and Administration Information

- Monitor patients closely for respiratory depression when initiating therapy and following dosage increases with ULTIVA and adjust the dosage accordingly [see Warnings and Precautions (5.2)].
- ULTIVA is for IV use only.
- ULTIVA should not be administered without dilution.
- Continuous infusions of ULTIVA should be administered only by an infusion device. IV bolus administration of ULTIVA should be used only during the maintenance of general anesthesia. In nonintubated patients, single doses of ULTIVA should be administered over 30 to 60 seconds.
- Interruption of an infusion of ULTIVA will result in rapid offset of effect. Rapid clearance and lack of drug accumulation result in rapid dissipation of respiratory depressant and analgesic effects upon discontinuation of ULTIVA at recommended doses. Discontinuation of an infusion of ULTIVA should be preceded by the establishment of adequate postoperative analgesia.
- Injections of ULTIVA should be made into IV tubing at or close to the venous cannula. Upon discontinuation of ULTIVA, the IV tubing should be cleared to prevent the inadvertent administration of ULTIVA at a later point in time. Failure to adequately clear the IV tubing to remove residual ULTIVA has been associated with the appearance of respiratory depression, apnea, and muscle rigidity upon the administration of additional fluids or medications through the same IV tubing.
- Consider an alternative to ULTIVA for patients taking mixed agonist/antagonist and partial agonist opioid analgesics due to reduced analgesic effect or potential withdrawal symptoms. If concomitant use is warranted, carefully observe the patient, particularly during treatment initiation and dose adjustment. Discontinue ULTIVA if patient is not responding appropriately to treatment.
- Discard unused portion.

2.2 General Anesthesia

ULTIVA is not recommended as the sole agent in general anesthesia because loss of consciousness cannot be assured and because of a high incidence of apnea, muscle rigidity, and tachycardia. ULTIVA is synergistic with other anesthetics; therefore, clinicians may need to reduce doses of thiopental, propofol, isoflurane, and midazolam by up to 75% with the coadministration of ULTIVA. The administration of ULTIVA must be individualized based on the patient's response.

Induction of Anesthesia

ULTIVA should be administered at an infusion rate of 0.5 to 1 mcg/kg/min with a hypnotic or volatile agent for the induction of anesthesia. If endotracheal intubation is to occur less than 8 minutes after the start of the infusion of ULTIVA, then an initial dose of 1 mcg/kg may be administered over 30 to 60 seconds.

ULTIVA should not be used as a sole agent for induction of anesthesia because loss of consciousness cannot be assured and because of a high incidence of apnea, muscle rigidity, and tachycardia.

Maintenance of Anesthesia

After endotracheal intubation, the infusion rate of ULTIVA should be decreased in accordance with the dosing guidelines in Tables 1 (adults, predominately ASA physical status I, II, or III) and 2 (pediatric patients).

- Due to the fast onset and short duration of action of ULTIVA, the rate of administration during anesthesia can be titrated upward in 25% to 100% increments in adult patients or up to 50% increments in pediatric patients, or downward in 25% to 50% decrements every 2 to 5 minutes to attain the desired level of µ-opioid effect.
- In response to light anesthesia or transient episodes of intense surgical stress, supplemental bolus doses of 1 mcg/kg may be administered every 2 to 5 minutes.
- At infusion rates > 1 mcg/kg/min, increases in the concomitant anesthetic agents should be considered to increase the depth of anesthesia. [See Clinical Pharmacology: Specific Populations: Pediatric Population (12.3) and Dosage and Administration, Table 2 (2.2).]

Table 1: Dosing Guidelines in Adults – General Anesthesia and Continuing as an Analgesic into the Postoperative Care Unit or Intensive Care Setting [An initial dose of 1 mcg/kg may be administered over 30 to 60 seconds.]
Phase | Continuous IV Infusion of; ULTIVA (mcg/kg/min) | Range of Infusion Dose; ULTIVA (mcg/kg/min) | Supplemental IV Bolus Dose of ULTIVA; (mcg/kg)
Induction of Anesthesia (through intubation) | 0.5 – 1
Maintenance of anesthesia with:
Nitrous oxide (66%) | 0.4 | 0.1 – 2 | 1
Isoflurane (0.4 to 1.5 MAC) | 0.25 | 0.05 – 2 | 1
Propofol (100 to 200 mcg/kg/min) | 0.25 | 0.05 – 2 | 1
Continuation as an analgesic into the immediate postoperative period | 0.1 | 0.025 – 0.2 | not recommended

Table 2 summarizes the recommended doses in pediatric patients, predominantly ASA physical status I, II, or III. In pediatric patients, remifentanil was administered with nitrous oxide or nitrous oxide in combination with halothane, sevoflurane, or isoflurane. The use of atropine may blunt the potential for bradycardia that can occur upon administration of ULTIVA.

Table 2: Dosing Guidelines in Pediatric Patients – Maintenance of Anesthesia
Phase | Continuous IV Infusion of; ULTIVA (mcg/kg/min) | Range of Infusion Dose; ULTIVA (mcg/kg/min) | Supplemental IV Bolus Dose of ULTIVA; (mcg/kg)
Maintenance of anesthesia in patients aged 1 to 12 years old with [An initial dose of 1 mcg/kg may be administered over 30 to 60 seconds.] :
Halothane (0.3 to 1.5 MAC) | 0.25 | 0.05 – 1.3 | 1
Sevoflurane (0.3 to 1.5 MAC) | 0.25 | 0.05 – 1.3 | 1
Isoflurane (0.4 to 1.5 MAC) | 0.25 | 0.05 – 1.3 | 1
Maintenance of anesthesia for patients from birth to 2 months of age with:
Nitrous oxide (70%) [The clearance rate in neonates is highly variable, on average two times higher than in the young healthy adult population. Therefore, an increased infusion rate may be necessary to maintain adequate surgical anesthesia, and additional bolus doses may be required. The use of atropine may blunt the potential for bradycardia that can occur upon administration of ULTIVA. [See Clinical Pharmacology: Specific Populations: Pediatric Population (12.3) and Clinical Studies (14.4).]] | 0.4 | 0.4 – 1.0 | 1 [Boluses of 1 mcg/kg were studied in ASA 1 and 2, full-term patients weighing at least 2500 gm, undergoing pyloromyotomy who received pretreatment with atropine. Neonates receiving supplementation with potent inhalation agents or neuraxial anesthesia, those with significant co-morbidities or undergoing significant fluid shifts, or those who have not been pretreated with atropine, may require smaller bolus doses to avoid hypotension and/or bradycardia.]

2.3 Continuation as an Analgesic into the Immediate Postoperative Period Under the Direct Supervision of an Anesthesia Practitioner

Infusions of ULTIVA may be continued into the immediate postoperative period for select patients for whom later transition to longer acting analgesics may be desired.

- ULTIVA has not been studied in pediatric patients for use in the immediate postoperative period.
- The use of bolus injections of ULTIVA to treat pain during the postoperative period is not recommended.
- When used as an IV analgesic in the immediate postoperative period, ULTIVA should be initially administered by continuous infusion at a rate of 0.1 mcg/kg/min.
- The infusion rate may be adjusted every 5 minutes in 0.025 mcg/kg/min increments to balance the patient's level of analgesia and respiratory rate.
- Infusion rates greater than 0.2 mcg/kg/min are associated with respiratory depression (respiratory rate less than 8 breaths/min).

Due to the rapid offset of action of ULTIVA, no residual analgesic activity will be present within 5 to 10 minutes after discontinuation. For patients undergoing surgical procedures where postoperative pain is generally anticipated, alternative analgesics should be administered prior to discontinuation of ULTIVA. The choice of analgesic should be appropriate for the patient's surgical procedure and the level of follow-up care [see Clinical Studies (14)].

2.4 Analgesic Component of Monitored Anesthesia Care

It is strongly recommended that supplemental oxygen be supplied to the patient whenever ULTIVA is administered.

- ULTIVA has not been studied for use in children in monitored anesthesia care.

Single Dose

A single IV dose of 0.5 to 1 mcg/kg over 30 to 60 seconds of ULTIVA may be given 90 seconds before the placement of the local or regional anesthetic block [see Warnings and Precautions (5.6)].

Continuous Infusion

When used alone as an IV analgesic component of monitored anesthesia care, ULTIVA should be initially administered by continuous infusion at a rate of 0.1 mcg/kg/min beginning 5 minutes before placement of the local or regional anesthetic block.

- Because of the risk for hypoventilation, the infusion rate of ULTIVA should be decreased to 0.05 mcg/kg/min following placement of the block.
- Thereafter, rate adjustments of 0.025 mcg/kg/min at 5 minute intervals may be used to balance the patient's level of analgesia and respiratory rate.
- Rates greater than 0.2 mcg/kg/min are generally associated with respiratory depression (respiratory rates less than 8 breaths/min).
- Bolus doses of ULTIVA administered simultaneously with a continuous infusion of ULTIVA to spontaneously breathing patients are not recommended.

Table 3 summarizes the recommended doses for monitored anesthesia care in adult patients, predominately ASA physical status I, II, or III.

Table 3: Dosing Guidelines in Adults – Monitored Anesthesia Care
Method | Timing | ULTIVA Alone | ULTIVA + 2 mg Midazolam
Single IV Dose | Given 90 seconds before local anesthetic | 1 mcg/kg over 30 to 60 seconds | 0.5 mcg/kg over 30 to 60 seconds
Continuous IV Infusion | Beginning 5 minutes before local anesthetic | 0.1 mcg/kg/min | 0.05 mcg/kg/min
Continuous IV Infusion | After local anesthetic | 0.05 mcg/kg/min (Range: 0.025 to 0.2 mcg/kg/min) | 0.025 mcg/kg/min (Range: 0.025 to 0.2 mcg/kg/min)

2.5 Discontinuation

Upon discontinuation of ULTIVA, the IV tubing should be cleared to prevent the inadvertent administration of ULTIVA at a later time.

Interruption of an infusion of ULTIVA will result in rapid offset of effect. Rapid clearance and lack of drug accumulation result in rapid dissipation of respiratory depressant and analgesic effects upon discontinuation of ULTIVA at recommended doses. Discontinuation of an infusion of ULTIVA should be preceded by the establishment of adequate postoperative analgesia [see Warnings and Precautions (5.13)].

For patients undergoing surgical procedures where postoperative pain is generally anticipated, alternative analgesics should be administered prior to discontinuation of ULTIVA. The choice of analgesic should be appropriate for the patient's surgical procedure and the level of follow-up care [see Clinical Studies (14)].

2.6 Dosage Modifications in Geriatric Patients

The starting doses of ULTIVA should be decreased by 50% in elderly patients (> 65 years). ULTIVA should then be cautiously titrated to effect [see Use in Specific Populations (8.5)].

2.7 Dosage Modifications in Pediatric Patients

See Table 2 for dosing recommendations for use of ULTIVA in pediatric patients from birth to 12 years of age for maintenance of anesthesia. [See Clinical Pharmacology: Specific Populations: Pediatric Population (12.3) and Dosage and Administration, Table 2 and Maintenance of Anesthesia (2.2).]

ULTIVA has not been studied in pediatric patients for use in the immediate postoperative period or for use as a component of monitored anesthesia care.

2.8 Dosage Modifications in Coronary Artery Bypass Surgery

Table 4 summarizes the recommended doses for induction, maintenance, and continuation as an analgesic into the ICU in adult patients, predominantly ASA physical status III or IV. To avoid hypotension during the induction phase, it is important to consider the concomitant medication regimens. [See Clinical Studies: Coronary Artery Bypass Surgery (14.5).]

Table 4: Dosing Recommendations [See Clinical Studies: Coronary Artery Bypass Surgery subsection (14.5) for concomitant medication regimens.] – Coronary Artery Bypass Surgery
Phase | Continuous IV Infusion of ULTIVA (mcg/kg/min) | Range of Infusion Dose ULTIVA (mcg/kg/min) | Supplemental IV Bolus Dose of ULTIVA (mcg/kg)
Induction of Anesthesia (through intubation) | 1
Maintenance of Anesthesia | 1 | 0.125 to 4 | 0.5 to 1
Continuation as an analgesic into ICU | 1 | 0.05 to 1

2.9 Dosage Modifications in Obese Patients

The starting doses of ULTIVA should be based on ideal body weight (IBW) in obese patients (greater than 30% over their IBW) [see Use in Specific Populations (8.6)].

2.10 Dosage Modifications in Preanesthetic Medication

The need for premedication and the choice of anesthetic agents must be individualized. In clinical studies, patients who received ULTIVA frequently received a benzodiazepine premedication.

2.11 Preparation for Administration

To reconstitute solution, add 1 mL of diluent per mg of remifentanil. Shake well to dissolve. When reconstituted as directed, the solution contains approximately 1 mg of remifentanil activity per 1 mL.

- ULTIVA should be diluted to a recommended final concentration of 20, 25, 50, or 250 mcg/mL prior to administration (see Table 5). ULTIVA should not be administered without dilution.

Table 5: Reconstitution and Dilution of ULTIVA
Final Concentration | Amount of ULTIVA in Each Vial | Final Volume After Reconstitution and Dilution
20 mcg/mL | 1 mg | 50 mL
20 mcg/mL | 2 mg | 100 mL
20 mcg/mL | 5 mg | 250 mL
25 mcg/mL | 1 mg | 40 mL
25 mcg/mL | 2 mg | 80 mL
25 mcg/mL | 5 mg | 200 mL
50 mcg/mL | 1 mg | 20 mL
50 mcg/mL | 2 mg | 40 mL
50 mcg/mL | 5 mg | 100 mL
250 mcg/mL | 5 mg | 20 mL

Continuous IV infusions of ULTIVA should be administered only by an infusion device. Infusion rates of ULTIVA can be individualized for each patient using Table 6:

Table 6: IV Infusion Rates of ULTIVA (mL/kg/h)
Drug Delivery Rate (mcg/kg/min) | Infusion Delivery Rate (mL/kg/h)
Drug Delivery Rate (mcg/kg/min) | 20 mcg/mL | 25 mcg/mL | 50 mcg/mL | 250 mcg/mL
0.0125 | 0.038 | 0.03 | 0.015 | not recommended
0.025 | 0.075 | 0.06 | 0.03 | not recommended
0.05 | 0.15 | 0.12 | 0.06 | 0.012
0.075 | 0.23 | 0.18 | 0.09 | 0.018
0.1 | 0.3 | 0.24 | 0.12 | 0.024
0.15 | 0.45 | 0.36 | 0.18 | 0.036
0.2 | 0.6 | 0.48 | 0.24 | 0.048
0.25 | 0.75 | 0.6 | 0.3 | 0.06
0.5 | 1.5 | 1.2 | 0.6 | 0.12
0.75 | 2.25 | 1.8 | 0.9 | 0.18
1.0 | 3.0 | 2.4 | 1.2 | 0.24
1.25 | 3.75 | 3.0 | 1.5 | 0.3
1.5 | 4.5 | 3.6 | 1.8 | 0.36
1.75 | 5.25 | 4.2 | 2.1 | 0.42
2.0 | 6.0 | 4.8 | 2.4 | 0.48

When ULTIVA is used as an analgesic component of monitored analgesia care, a final concentration of 25 mcg/mL is recommended. When ULTIVA is used for pediatric patients 1 year of age and older, a final concentration of 20 or 25 mcg/mL is recommended. Table 7 is a guideline for milliliter-per-hour delivery for a solution of 20 mcg/mL with an infusion device.

Table 7: IV Infusion Rates of ULTIVA (mL/h) for a 20 mcg/mL Solution
Infusion Rate (mcg/kg/min) | Patient Weight (kg)
Infusion Rate (mcg/kg/min) | 5 | 10 | 20 | 30 | 40 | 50 | 60
0.0125 | 0.188 | 0.375 | 0.75 | 1.125 | 1.5 | 1.875 | 2.25
0.025 | 0.375 | 0.75 | 1.5 | 2.25 | 3.0 | 3.75 | 4.5
0.05 | 0.75 | 1.5 | 3.0 | 4.5 | 6.0 | 7.5 | 9.0
0.075 | 1.125 | 2.25 | 4.5 | 6.75 | 9.0 | 11.25 | 13.5
0.1 | 1.5 | 3.0 | 6.0 | 9.0 | 12.0 | 15.0 | 18.0
0.15 | 2.25 | 4.5 | 9.0 | 13.5 | 18.0 | 22.5 | 27.0
0.2 | 3.0 | 6.0 | 12.0 | 18.0 | 24.0 | 30.0 | 36.0
0.25 | 3.75 | 7.5 | 15.0 | 22.5 | 30.0 | 37.5 | 45.0
0.3 | 4.5 | 9.0 | 18.0 | 27.0 | 36.0 | 45.0 | 54.0
0.35 | 5.25 | 10.5 | 21.0 | 31.5 | 42.0 | 52.5 | 63.0
0.4 | 6.0 | 12.0 | 24.0 | 36.0 | 48.0 | 60.0 | 72.0

Table 8 is a guideline for milliliter-per-hour delivery for a solution of 25 mcg/mL with an infusion device.

Table 8: IV Infusion Rates of ULTIVA (mL/h) for a 25 mcg/mL Solution
Infusion Rate (mcg/kg/min) | Patient Weight (kg)
Infusion Rate (mcg/kg/min) | 10 | 20 | 30 | 40 | 50 | 60 | 70 | 80 | 90 | 100
0.0125 | 0.3 | 0.6 | 0.9 | 1.2 | 1.5 | 1.8 | 2.1 | 2.4 | 2.7 | 3.0
0.025 | 0.6 | 1.2 | 1.8 | 2.4 | 3.0 | 3.6 | 4.2 | 4.8 | 5.4 | 6.0
0.05 | 1.2 | 2.4 | 3.6 | 4.8 | 6.0 | 7.2 | 8.4 | 9.6 | 10.8 | 12.0
0.075 | 1.8 | 3.6 | 5.4 | 7.2 | 9.0 | 10.8 | 12.6 | 14.4 | 16.2 | 18.0
0.1 | 2.4 | 4.8 | 7.2 | 9.6 | 12.0 | 14.4 | 16.8 | 19.2 | 21.6 | 24.0
0.15 | 3.6 | 7.2 | 10.8 | 14.4 | 18.0 | 21.6 | 25.2 | 28.8 | 32.4 | 36.0
0.2 | 4.8 | 9.6 | 14.4 | 19.2 | 24.0 | 28.8 | 33.6 | 38.4 | 43.2 | 48.0

Table 9 is a guideline for milliliter-per-hour delivery for a solution of 50 mcg/mL with an infusion device.

Table 9: IV Infusion Rates of ULTIVA (mL/h) for a 50 mcg/mL Solution
Infusion Rate (mcg/kg/min) | Patient Weight (kg)
Infusion Rate (mcg/kg/min) | 30 | 40 | 50 | 60 | 70 | 80 | 90 | 100
0.025 |  |  |  |  | 2.1 | 2.4 | 2.7 | 3.0
0.05 |  | 2.4 | 3.0 | 3.6 | 4.2 | 4.8 | 5.4 | 6.0
0.075 | 2.7 | 3.6 | 4.5 | 5.4 | 6.3 | 7.2 | 8.1 | 9.0
0.1 | 3.6 | 4.8 | 6.0 | 7.2 | 8.4 | 9.6 | 10.8 | 12.0
0.15 | 5.4 | 7.2 | 9.0 | 10.8 | 12.6 | 14.4 | 16.2 | 18.0
0.2 | 7.2 | 9.6 | 12.0 | 14.4 | 16.8 | 19.2 | 21.6 | 24.0
0.25 | 9.0 | 12.0 | 15.0 | 18.0 | 21.0 | 24.0 | 27.0 | 30.0
0.5 | 18.0 | 24.0 | 30.0 | 36.0 | 42.0 | 48.0 | 54.0 | 60.0
0.75 | 27.0 | 36.0 | 45.0 | 54.0 | 63.0 | 72.0 | 81.0 | 90.0
1.0 | 36.0 | 48.0 | 60.0 | 72.0 | 84.0 | 96.0 | 108.0 | 120.0
1.25 | 45.0 | 60.0 | 75.0 | 90.0 | 105.0 | 120.0 | 135.0 | 150.0
1.5 | 54.0 | 72.0 | 90.0 | 108.0 | 126.0 | 144.0 | 162.0 | 180.0
1.75 | 63.0 | 84.0 | 105.0 | 126.0 | 147.0 | 168.0 | 189.0 | 210.0
2.0 | 72.0 | 96.0 | 120.0 | 144.0 | 168.0 | 192.0 | 216.0 | 240.0

Table 10 is a guideline for milliliter-per-hour delivery for a solution of 250 mcg/mL with an infusion device.

Table 10: IV Infusion Rates of ULTIVA (mL/h) for a 250 mcg/mL Solution
Infusion Rate (mcg/kg/min) | Patient Weight (kg)
Infusion Rate (mcg/kg/min) | 30 | 40 | 50 | 60 | 70 | 80 | 90 | 100
0.1 | 0.72 | 0.96 | 1.20 | 1.44 | 1.68 | 1.92 | 2.16 | 2.40
0.15 | 1.08 | 1.44 | 1.80 | 2.16 | 2.52 | 2.88 | 3.24 | 3.60
0.2 | 1.44 | 1.92 | 2.40 | 2.88 | 3.36 | 3.84 | 4.32 | 4.80
0.25 | 1.80 | 2.40 | 3.00 | 3.60 | 4.20 | 4.80 | 5.40 | 6.00
0.5 | 3.60 | 4.80 | 6.00 | 7.20 | 8.40 | 9.60 | 10.80 | 12.00
0.75 | 5.40 | 7.20 | 9.00 | 10.80 | 12.60 | 14.40 | 16.20 | 18.00
1.0 | 7.20 | 9.60 | 12.00 | 14.40 | 16.80 | 19.20 | 21.60 | 24.00
1.25 | 9.00 | 12.00 | 15.00 | 18.00 | 21.00 | 24.00 | 27.00 | 30.00
1.5 | 10.80 | 14.40 | 18.00 | 21.60 | 25.20 | 28.80 | 32.40 | 36.00
1.75 | 12.60 | 16.80 | 21.00 | 25.20 | 29.40 | 33.60 | 37.80 | 42.00
2.0 | 14.40 | 19.20 | 24.00 | 28.80 | 33.60 | 38.40 | 43.20 | 48.00

2.12 Compatibility and Stability

Reconstitution and Dilution Prior to Administration

ULTIVA is stable for 24 hours at room temperature after reconstitution and further dilution to concentrations of 20 to 250 mcg/mL with the IV fluids listed below.

Sterile Water for Injection, USP
5% Dextrose Injection, USP
5% Dextrose and 0.9% Sodium Chloride Injection, USP
0.9% Sodium Chloride Injection, USP
0.45% Sodium Chloride Injection, USP
Lactated Ringer's and 5% Dextrose Injection, USP

ULTIVA is stable for 4 hours at room temperature after reconstitution and further dilution to concentrations of 20 to 250 mcg/mL with Lactated Ringer's Injection, USP.

ULTIVA has been shown to be compatible with these IV fluids when coadministered into a running IV administration set.

Compatibility with Other Therapeutic Agents

ULTIVA has been shown to be compatible with Diprivan® (propofol) Injection when coadministered into a running IV administration set. The compatibility of ULTIVA with other therapeutic agents has not been evaluated.

Incompatibilities

Nonspecific esterases in blood products may lead to the hydrolysis of remifentanil to its carboxylic acid metabolite. Therefore, administration of ULTIVA into the same IV tubing with blood is not recommended.

Note: Parenteral drug products should be inspected visually for particulate matter and discoloration prior to administration whenever solution and container permit. Product should be a clear, colorless liquid after reconstitution and free of visible particulate matter.

ULTIVA does not contain any antimicrobial preservative and thus care must be taken to assure the sterility of prepared solutions.

3 DOSAGE FORMS AND STRENGTHS

For injection: 1 mg, 2 mg, and 5 mg:

3 mL Vial | 1 mg lyophilized powder
5 mL Vial | 2 mg lyophilized powder
10 mL Vial | 5 mg lyophilized powder

4 CONTRAINDICATIONS

ULTIVA is contraindicated:

- For epidural or intrathecal administration due to the presence of glycine in the formulation [see Nonclinical Toxicology (13)].
- In patients with hypersensitivity to remifentanil (e.g., anaphylaxis) [see Adverse Reactions (6.2)].

5 WARNINGS AND PRECAUTIONS

5.1 Addiction, Abuse, and Misuse

ULTIVA contains remifentanil, a Schedule II controlled substance. As an opioid, ULTIVA exposes users to the risks of addiction, abuse, and misuse [see Drug Abuse and Dependence (9)].

Opioids are sought for nonmedical use and are subject to diversion from legitimate prescribed use. Consider these risks when handling ULTIVA. Strategies to reduce these risks include proper product storage and control practices for a C-II drug. Contact local state professional licensing board or state-controlled substances authority for information on how to prevent and detect abuse or diversion of this product.

5.2 Life-Threatening Respiratory Depression

Serious, life-threatening, or fatal respiratory depression has been reported with the use of opioids, even when used as recommended. Respiratory depression, if not immediately recognized and treated, may lead to respiratory arrest and death.

ULTIVA should be administered only by persons specifically trained in the use of anesthetic drugs and the management of the respiratory effects of potent opioids, including respiration and cardiac resuscitation of patients in the age group being treated. Such training must include the establishment and maintenance of a patent airway and assisted ventilation. Resuscitative and intubation equipment, oxygen, and opioid overdose reversal agents (e.g., naloxone, nalmefene) must be readily available.

Respiratory depression in spontaneously breathing patients is generally managed by decreasing the rate of the infusion of ULTIVA by 50% or by temporarily discontinuing the infusion [see Overdosage (10)].

Carbon dioxide (CO2) retention from opioid-induced respiratory depression can exacerbate the sedating effects of opioids. While serious, life-threatening, or fatal respiratory depression can occur at any time during the use of ULTIVA, the risk is greatest during the initiation of therapy or following a dosage increase. Monitor patients closely for respiratory depression, especially when initiating therapy with and following dosage increases of ULTIVA.

ULTIVA should not be used in diagnostic or therapeutic procedures outside the monitored anesthesia care setting. Patients receiving monitored anesthesia care should be continuously monitored by persons not involved in the conduct of the surgical or diagnostic procedure. Oxygen saturation should be monitored on a continuous basis.

Patients with significant chronic obstructive pulmonary disease or cor pulmonale, and those with a substantially decreased respiratory reserve, hypoxia, hypercapnia, or pre-existing respiratory depression are at increased risk of decreased respiratory drive including apnea, even at recommended dosages of ULTIVA. Elderly, cachectic, or debilitated patients may have altered pharmacokinetics or altered clearance compared to younger, healthier patients resulting in greater risk for respiratory depression. Monitor such patients closely including vital signs, particularly when initiating and titrating ULTIVA and when ULTIVA is given concomitantly with other drugs that depress respiration. To reduce the risk of respiratory depression, proper dosing and titration of ULTIVA are essential [see Dosage and Administration (2.11)].

5.3 Risks from Use as Postoperative Analgesia with Concomitant Benzodiazepines or Other CNS Depressants

When benzodiazepines or other CNS depressants are used with ULTIVA, pulmonary arterial pressure may be decreased. This fact should be considered by those who conduct diagnostic and surgical procedures where interpretation of pulmonary arterial pressure measurements might determine final management of the patient. When high dose or anesthetic dosages of ULTIVA are employed, even relatively small dosages of diazepam may cause cardiovascular depression.

When ULTIVA is used with CNS depressants, hypotension can occur. If it occurs, consider the possibility of hypovolemia and manage with appropriate parenteral fluid therapy. When operative conditions permit, consider repositioning the patient to improve venous return to the heart. Exercise care in moving and repositioning of patients because of the possibility of orthostatic hypotension. If volume expansion with fluids plus other countermeasures do not correct hypotension, consider administration of pressor agents other than epinephrine. Epinephrine may paradoxically decrease blood pressure in patients treated with a neuroleptic that blocks alpha adrenergic activity.

Hypotension, profound sedation, respiratory depression, coma, and death may result from the concomitant use of ULTIVA with benzodiazepines and/or other CNS depressants, including alcohol (e.g., non-benzodiazepine sedatives/hypnotics, anxiolytics, tranquilizers, muscle relaxants, general anesthetics, antipsychotics, gabapentinoids [gabapentin and pregabalin], and other opioids). Patients should be advised to avoid alcohol for 24 hours after surgery [see Drug Interactions (7)].

Observational studies have demonstrated that concomitant use of opioid analgesics and benzodiazepines increases the risk of drug-related mortality compared to use of opioid analgesics alone. Because of similar pharmacological properties, it is reasonable to expect similar risk with the concomitant use of other CNS depressant drugs with opioid analgesics [see Drug Interactions (7)].

If the decision is made to manage postoperative pain with ULTIVA concomitantly with a benzodiazepine or other CNS depressant, start dosing with the lowest effective dosage and titrate based on clinical response. Monitor patients closely for signs and symptoms of respiratory depression, sedation, and hypotension. Fluids or other measures to counter hypotension should be available [see Drug Interactions (7)].

5.4 Opioid-Induced Hyperalgesia and Allodynia

Opioid-Induced Hyperalgesia (OIH) occurs when an opioid analgesic paradoxically causes an increase in pain, or an increase in sensitivity to pain. This condition differs from tolerance, which is the need for increasing doses of opioids to maintain a defined effect [see Dependence (9.3)]. Symptoms of OIH include (but may not be limited to) increased levels of pain upon opioid dosage increase, decreased levels of pain upon opioid dosage decrease, or pain from ordinarily non-painful stimuli (allodynia). These symptoms may suggest OIH only if there is no evidence of underlying disease progression, opioid tolerance, opioid withdrawal, or addictive behavior.

Cases of OIH have been reported, both with short-term and longer-term use of opioid analgesics. Though the mechanism of OIH is not fully understood, multiple biochemical pathways have been implicated. Medical literature suggests a strong biologic plausibility between opioid analgesics and OIH and allodynia. If a patient is suspected to be experiencing OIH, carefully consider appropriately decreasing the dose of the current opioid analgesic or opioid rotation (safely switching the patient to a different opioid moiety) [see Dosage and Administration (2), Warnings and Precautions (5.2)].

5.5 Serotonin Syndrome with Concomitant Use of Serotonergic Drugs

Cases of serotonin syndrome, a potentially life-threatening condition, have been reported during concomitant use of ULTIVA with serotonergic drugs. Serotonergic drugs include selective serotonin reuptake inhibitors (SSRIs), serotonin and norepinephrine reuptake inhibitors (SNRIs), tricyclic antidepressants (TCAs), triptans, 5-HT3 receptor antagonists, drugs that affect the serotonergic neurotransmitter system (e.g., mirtazapine, trazodone, tramadol), certain muscle relaxants (i.e., cyclobenzaprine, metaxalone), and drugs that impair metabolism of serotonin (including MAO inhibitors, both those intended to treat psychiatric disorders and also others, such as linezolid and intravenous methylene blue) [see Drug Interactions (7)]. This may occur within the recommended dosage range.

Serotonin syndrome symptoms may include mental status changes (e.g., agitation, hallucinations, coma), autonomic instability (e.g., tachycardia, labile blood pressure, hyperthermia), neuromuscular aberrations (e.g., hyperreflexia, incoordination, rigidity), and/or gastrointestinal symptoms (e.g., nausea, vomiting, diarrhea) and can be fatal. The onset of symptoms generally occurs within several hours to a few days of concomitant use, but may occur later than that. Discontinue ULTIVA if serotonin syndrome is suspected.

5.6 Skeletal Muscle Rigidity

Skeletal muscle rigidity can be caused by ULTIVA and is related to the dose and speed of administration. ULTIVA may cause chest wall rigidity (inability to ventilate) after single doses of > 1 mcg/kg administered over 30 to 60 seconds, or after infusion rates > 0.1 mcg/kg/min. Single doses < 1 mcg/kg may cause chest wall rigidity when given concurrently with a continuous infusion of ULTIVA.

Muscle rigidity induced by ULTIVA should be managed in the context of the patient's clinical condition. Muscle rigidity occurring during the induction of anesthesia should be treated by the administration of a neuromuscular blocking agent and the concurrent induction medications and can be treated by decreasing the rate or discontinuing the infusion of ULTIVA or by administering a neuromuscular blocking agent. The neuromuscular blocking agents used should be compatible with the patient's cardiovascular status.

Muscle rigidity seen during the use of ULTIVA in spontaneously breathing patients may be treated by stopping or decreasing the rate of administration of ULTIVA. Resolution of muscle rigidity after discontinuing the infusion of ULTIVA occurs within minutes. In the case of life-threatening muscle rigidity, a rapid onset neuromuscular blocker or naloxone may be administered.

5.7 Potential Inactivation by Nonspecific Esterases in Blood Products

ULTIVA should not be administered into the same IV tubing with blood due to potential inactivation by nonspecific esterases in blood products.

5.8 Bradycardia

Bradycardia has been reported with ULTIVA and is responsive to ephedrine or anticholinergic drugs, such as atropine and glycopyrrolate.

5.9 Hypotension

Hypotension has been reported with ULTIVA and is responsive to decreases in the administration of ULTIVA or to IV fluids or catecholamine (ephedrine, epinephrine, norepinephrine, etc.) administration.

5.10 Intraoperative Awareness

Intraoperative awareness has been reported in patients under 55 years of age when ULTIVA has been administered with propofol infusion rates of ≤ 75 mcg/kg/min.

5.11 Risks of Use in Spontaneously Breathing Patients with Increased Intracranial Pressure, Brain Tumors, Head Injury, or Impaired Consciousness

In patients who may be susceptible to the intracranial effects of CO2 retention (e.g., those with evidence of increased intracranial pressure or brain tumors), ULTIVA may reduce respiratory drive, and the resultant CO2 retention can further increase intracranial pressure in spontaneously breathing patients. Monitor such patients for signs of sedation and respiratory depression, particularly when initiating therapy with ULTIVA.

Opioids may also obscure the clinical course in a patient with a head injury.

5.12 Risks of Use in Patients with Biliary Tract Disease

The remifentanil in ULTIVA may cause spasm of the sphincter of Oddi. Opioids may cause increases in serum amylase. Monitor patients with biliary tract disease, including acute pancreatitis, for worsening symptoms.

5.13 Increased Risk of Seizures in Patients with Seizure Disorders

The remifentanil in ULTIVA may increase the frequency of seizures in patients with seizure disorders, and may increase the risk of seizures occurring in other clinical settings associated with seizures. Monitor patients with a history of seizure disorders for worsened seizure control during ULTIVA therapy.

5.14 Rapid Offset of Action

Analgesic activity will subside within 5 to 10 minutes after discontinuation of administration of ULTIVA. However, respiratory depression may continue in some patients for up to 30 minutes after termination of infusion due to residual effects of concomitant anesthetics. Standard monitoring should be maintained in the postoperative period to ensure adequate recovery without stimulation. For patients undergoing surgical procedures where postoperative pain is generally anticipated, other analgesics should be administered prior to the discontinuation of ULTIVA.

6 ADVERSE REACTIONS

The following serious adverse reactions are described, or described in greater detail, in other sections:

- Addiction, Abuse, and Misuse [see Warnings and Precautions (5.1)]
- Life-Threatening Respiratory Depression [see Warnings and Precautions (5.2)]
- Interactions with Benzodiazepines or other CNS Depressants [see Warnings and Precautions (5.3)]
- Opioid-Induced Hyperalgesia and Allodynia [see Warnings and Precautions (5.4)]
- Serotonin Syndrome [see Warnings and Precautions (5.5)]
- Skeletal Muscle Rigidity [see Warnings and Precautions (5.6)]
- Bradycardia [see Warnings and Precautions (5.8)]
- Hypotension [see Warnings and Precautions (5.9)]
- Biliary Tract Disease [see Warnings and Precautions (5.12)]
- Seizures [see Warnings and Precautions (5.13)]

6.1 Clinical Trials Experience

Because clinical trials are conducted under widely varying conditions, adverse reaction rates observed in the clinical trials of a drug cannot be directly compared to rates in the clinical trials of another drug and may not reflect the rates observed in practice.

Adverse event information is derived from controlled clinical studies that were conducted in a variety of surgical procedures of varying duration, using a variety of premedications and other anesthetics, and in patient populations with diverse characteristics including underlying disease.

Adults

Approximately 2,770 adult patients were exposed to ULTIVA in controlled clinical studies. The frequencies of adverse events during general anesthesia with the recommended doses of ULTIVA are given in Table 11. Each patient was counted once for each type of adverse event.

Table 11: Adverse Events Reported in ≥ 1% of Adult Patients in General Anesthesia Studies [Does not include adverse events from cardiac studies or the neonatal study. See Tables 14, 15, and 16 for cardiac information.] at the Recommended Doses [See Table 1 for recommended doses. Not all doses of ULTIVA were equipotent to the comparator opioid. Administration of ULTIVA in excess of the recommended dose (i.e., doses > 1 and up to 20 mcg/kg) resulted in a higher incidence of some adverse events: muscle rigidity (37%), bradycardia (12%), hypertension (4%), and tachycardia (4%).] of ULTIVA
Adverse Event | Induction/Maintenance |  | Postoperative Analgesia |  | After Discontinuation
Adverse Event | ULTIVA (n = 921) | Alfentanil/ Fentanyl (n = 466) | ULTIVA (n = 281) | Morphine (n = 98) | ULTIVA (n = 929) | Alfentanil/Fentanyl (n = 466)
Nausea | 8 (< 1%) | 0 | 61 (22%) | 15 (15%) | 339 (36%) | 202 (43%)
Hypotension | 178 (19%) | 30 (6%) | 0 | 0 | 16 (2%) | 9 (2%)
Vomiting | 4 (< 1%) | 1 (< 1%) | 22 (8%) | 5 (5%) | 150 (16%) | 91 (20%)
Muscle rigidity | 98 (11%) [Included in the muscle rigidity incidence is chest wall rigidity (5%). The overall muscle rigidity incidence is < 1% when remifentanil is administered concurrently or after a hypnotic induction agent.] | 37 (8%) | 7 (2%) | 0 | 2 (< 1%) | 1 (< 1%)
Bradycardia | 62 (7%) | 24 (5%) | 3 (1%) | 3 (3%) | 11 (1%) | 6 (1%)
Shivering | 3 (< 1%) | 0 | 15 (5%) | 9 (9%) | 49 (5%) | 10 (2%)
Fever | 1 (< 1%) | 0 | 2 (< 1%) | 0 | 44 (5%) | 9 (2%)
Dizziness | 0 | 0 | 1 (< 1%) | 0 | 27 (3%) | 9 (2%)
Visual disturbance | 0 | 0 | 0 | 0 | 24 (3%) | 14 (3%)
Headache | 0 | 0 | 1 (< 1%) | 1 (1%) | 21 (2%) | 8 (2%)
Respiratory depression | 1 (< 1%) | 0 | 19 (7%) | 4 (4%) | 17 (2%) | 20 (4%)
Apnea | 0 | 1 (< 1%) | 9 (3%) | 2 (2%) | 2 (< 1%) | 1 (< 1%)
Pruritus | 2 (< 1%) | 0 | 7 (2%) | 1 (1%) | 22 (2%) | 7 (2%)
Tachycardia | 6 (< 1%) | 7 (2%) | 0 | 0 | 10 (1%) | 8 (2%)
Postoperative pain | 0 | 0 | 7 (2%) | 0 | 4 (< 1%) | 5 (1%)
Hypertension | 10 (1%) | 7 (2%) | 5 (2%) | 3 (3%) | 12 (1%) | 8 (2%)
Agitation | 2 (< 1%) | 0 | 3 (1%) | 1 (1%) | 6 (< 1%) | 1 (< 1%)
Hypoxia | 0 | 0 | 1 (< 1%) | 0 | 10 (1%) | 7 (2%)

In the elderly population (> 65 years), the incidence of hypotension is higher, whereas the incidence of nausea and vomiting is lower.

Table 12: Incidence (%) of Most Common Adverse Events by Gender in General Anesthesia Studies [Does not include adverse events from cardiac studies or the neonatal study.] at the Recommended Doses [See Table 1 for recommended doses. Not all doses of ULTIVA were equipotent to the comparator opioid.] of ULTIVA
Adverse Event; n | Induction Maintenance |  |  |  | Postoperative Analgesia |  |  |  | After Discontinuation
Adverse Event; n | ULTIVA |  | Alfentanil/Fentanyl |  | ULTIVA |  | Morphine |  | ULTIVA |  | Alfentanil/Fentanyl
Adverse Event; n | Male; 326 | Female; 595 | Male; 183 | Female; 283 | Male; 85 | Female; 196 | Male; 36 | Female; 62 | Male; 332 | Female; 597 | Male; 183 | Female; 283
Nausea | 2% | < 1% | 0 | 0 | 12% | 26% | 8% | 19% | 22% | 45% | 30% | 52%
Hypotension | 29% | 14% | 7% | 6% | 0 | 0 | 0 | 0 | 2% | 2% | 2% | 2%
Vomiting | < 1% | < 1% | 0 | < 1% | 4% | 10% | 0 | 8% | 5% | 22% | 8% | 27%
Muscle rigidity | 17% | 7% | 14% | 4% | 6% | 1% | 0 | 0 | < 1% | < 1% | 0 | < 1%

The frequencies of adverse events from the clinical studies at the recommended doses of ULTIVA in monitored anesthesia care are given in Table 13.

Table 13: Adverse Events Reported in ≥ 1% of Adult Patients in Monitored Anesthesia Care Studies at the Recommended Doses [See Table 3 for recommended doses. Administration of ULTIVA in excess of the recommended infusion rate (i.e., starting doses > 0.1 mcg/kg/min) resulted in a higher incidence of some adverse events: nausea (60%), apnea (8%), and muscle rigidity (5%).] of ULTIVA
Adverse Event | ULTIVA (n = 159) | ULTIVA + 2 mg Midazolam [With higher midazolam doses, higher incidences of respiratory depression and apnea were observed.] (n = 103) | Propofol (0.5 mg/kg then 50 mcg/kg/min) (n = 63)
Nausea | 70 (44%) | 19 (18%) | 20 (32%)
Vomiting | 35 (22%) | 5 (5%) | 13 (21%)
Pruritus | 28 (18%) | 16 (16%) | 0
Headache | 28 (18%) | 12 (12%) | 6 (10%)
Sweating | 10 (6%) | 0 | 1 (2%)
Shivering | 8 (5%) | 1 (< 1%) | 1 (2%)
Dizziness | 8 (5%) | 5 (5%) | 1 (2%)
Hypotension | 7 (4%) | 0 | 6 (10%)
Bradycardia | 6 (4%) | 0 | 7 (11%)
Respiratory depression | 4 (3%) | 1 (< 1%) | 0
Muscle rigidity | 4 (3%) | 0 | 1 (2%)
Chills | 2 (1%) | 0 | 2 (3%)
Flushing | 2 (1%) | 0 | 0
Warm sensation | 2 (1%) | 0 | 0
Pain at study IV site | 2 (1%) | 0 | 11 (17%)

Other Adverse Events in Adult Patients

The frequencies of less commonly reported adverse clinical events from all controlled general anesthesia and monitored anesthesia care studies are presented below.

Event frequencies are calculated as the number of patients who were administered ULTIVA and reported an event divided by the total number of patients exposed to ULTIVA in all controlled studies including cardiac dose-ranging and neurosurgery studies (n = 1,883 general anesthesia, n = 609 monitored anesthesia care).

Incidence Less than 1%

Digestive: constipation, abdominal discomfort, xerostomia, gastro-esophageal reflux, dysphagia, diarrhea, ileus.

Cardiovascular: various atrial and ventricular arrhythmias, heart block, ECG change consistent with myocardial ischemia, elevated CPK-MB level, syncope.

Musculoskeletal: muscle stiffness, musculoskeletal chest pain.

Respiratory: cough, dyspnea, bronchospasm, laryngospasm, rhonchi, stridor, nasal congestion, pharyngitis, pleural effusion, hiccup(s), pulmonary edema, rales, bronchitis, rhinorrhea.

Nervous: anxiety, involuntary movement, prolonged emergence from anesthesia, confusion, awareness under anesthesia without pain, rapid awakening from anesthesia, tremors, disorientation, dysphoria, nightmare(s), hallucinations, paresthesia, nystagmus, twitch, seizure, amnesia.

Body as a Whole: decreased body temperature, anaphylactic reaction, delayed recovery from neuromuscular block.

Skin: rash, urticaria.

Urogenital: urine retention, oliguria, dysuria, urine incontinence.

Infusion Site Reaction: erythema, pruritus, rash.

Metabolic and Nutrition: abnormal liver function, hyperglycemia, electrolyte disorders, increased CPK level.

Hematologic and Lymphatic: anemia, lymphopenia, leukocytosis, thrombocytopenia.

The frequencies of adverse events from the clinical studies at the recommended doses of ULTIVA in cardiac surgery are given in Tables 14, 15, and 16. These tables represent adverse events collected during discrete phases of cardiac surgery. Any event should be viewed as temporally associated with drug administration and the phase indicated should not be perceived as the only time the event might occur.

Table 14: Adverse Events Reported in ≥ 1% of Patients in the Induction/Intubation and Maintenance Phases of Cardiac Surgery Studies at the Recommended Doses [See Table 4 for recommended doses.] of ULTIVA
 | Induction/Intubation |  |  | Maintenance
Adverse Event | ULTIVA (n = 227) | Fentanyl (n = 176) | Sufentanil (n = 41) | ULTIVA (n = 227) | Fentanyl (n = 176) | Sufentanil (n = 41)
Hypotension | 18 (8%) | 6 (3%) | 7 (17%) | 26 (11%) | 6 (3%) | 1 (2%)
Bradycardia | 9 (4%) | 5 (3%) | 0 | 3 (1%) | 1 (< 1%) | 1 (2%)
Hypertension | 3 (1%) | 2 (1%) | 2 (5%) | 8 (4%) | 6 (3%) | 1 (2%)
Constipation | 9 (4%) | 1 (< 1%) | 3 (7%) | 0 | 0 | 1 (2%)
Muscle rigidity | 2 (< 1%) | 2 (1%) | 0 | 5 (2%) | 8 (5%) | 0
Premature ventricular beats | 1 (< 1%) | 0 | 0 | 3 (1%) | 1 (< 1%) | 0
Myocardial ischemia | 0 | 0 | 0 | 7 (3%) | 8 (5%) | 1 (2%)
Atrial fibrillation | 0 | 0 | 0 | 7 (3%) | 3 (2%) | 1 (2%)
Decreased cardiac output | 0 | 0 | 0 | 5 (2%) | 1 (< 1%) | 1 (2%)
Tachycardia | 0 | 1 (< 1%) | 0 | 4 (2%) | 2 (1%) | 0
Coagulation disorder | 0 | 0 | 0 | 4 (2%) | 0 | 1 (2%)
Arrhythmia | 0 | 0 | 0 | 3 (1%) | 0 | 0
Ventricular fibrillation | 0 | 0 | 0 | 3 (1%) | 1 (< 1%) | 1 (2%)
Postoperative complication | 0 | 0 | 0 | 3 (1%) | 0 | 0
Third degree heart block | 0 | 0 | 0 | 2 (< 1%) | 0 | 1 (2%)
Hemorrhage | 0 | 0 | 0 | 2 (< 1%) | 0 | 1 (2%)
Perioperative complication | 0 | 0 | 0 | 2 (< 1%) | 1 (< 1%) | 1 (2%)
Involuntary movement(s) | 0 | 0 | 0 | 2 (< 1%) | 3 (2%) | 0
Thrombocytopenia | 0 | 0 | 1 (2%) | 0 | 0 | 0
Oliguria | 0 | 0 | 0 | 0 | 3 (2%) | 0
Anemia | 0 | 0 | 0 | 2 (< 1%) | 2 (1%) | 0

Table 15: Adverse Events Reported in ≥ 1% of Patients in the ICU Phase of Cardiac Surgery Studies at the Recommended Doses [See Table 4 for recommended doses.] of ULTIVA
Adverse Event | ULTIVA n = 227 | Fentanyl n = 176 | Sufentanil n = 41
Hypertension | 14 (6%) | 8 (5%) | 2 (5%)
Hypotension | 12 (5%) | 3 (2%) | 1 (2%)
Tachycardia | 9 (4%) | 5 (3%) | 0
Shivering | 8 (4%) | 3 (2%) | 1 (2%)
Nausea | 8 (4%) | 3 (2%) | 0
Hemorrhage | 4 (2%) | 1 (< 1%) | 1 (2%)
Postoperative complication | 4 (2%) | 5 (3%) | 2 (5%)
Agitation | 4 (2%) | 1 (< 1%) | 1 (2%)
Ache | 4 (2%) | 0 | 0
Decreased cardiac output | 3 (1%) | 0 | 0
Arrhythmia | 3 (1%) | 0 | 0
Muscle rigidity | 2 (< 1%) | 1 (< 1%) | 2 (5%)
Bradycardia | 2 (< 1%) | 2 (1%) | 0
Vomiting | 1 (< 1%) | 2 (1%) | 0
Premature ventricular beats | 1 (< 1%) | 2 (1%) | 0
Anemia | 0 | 3 (2%) | 0
Somnolence | 0 | 0 | 1 (2%)
Fever | 0 | 2 (1%) | 0

Table 16: Adverse Events Reported in ≥ 1% of Patients in the Post-Study Drug Phase of Cardiac Surgery Studies at the Recommended Doses [See Table 4 for recommended doses.] of ULTIVA
Adverse Event | ULTIVA n = 227 | Fentanyl n = 176 | Sufentanil n = 41
Nausea | 90 (40%) | 63 (36%) | 16 (39%)
Vomiting | 33 (15%) | 26 (15%) | 3 (7%)
Fever | 30 (13%) | 15 (9%) | 0
Atrial fibrillation | 27 (12%) | 33 (19%) | 4 (10%)
Constipation | 20 (9%) | 35 (20%) | 3 (7%)
Pleural effusion | 11 (5%) | 2 (1%) | 2 (5%)
Hypotension | 8 (4%) | 8 (5%) | 1 (2%)
Tachycardia | 9 (4%) | 15 (9%) | 0
Postoperative complication | 10 (4%) | 6 (3%) | 2 (5%)
Oliguria | 7 (3%) | 7 (4%) | 1 (2%)
Confusion | 7 (3%) | 10 (6%) | 5 (12%)
Ache | 6 (3%) | 2 (1%) | 0
Anxiety | 6 (3%) | 6 (3%) | 0
Headache | 6 (3%) | 2 (1%) | 0
Perioperative complication | 5 (2%) | 7 (4%) | 1 (2%)
Anemia | 5 (2%) | 5 (3%) | 1 (2%)
Agitation | 5 (2%) | 3 (2%) | 1 (2%)
Diarrhea | 5 (2%) | 1 (< 1%) | 1 (2%)
Edema | 4 (2%) | 6 (3%) | 0
Dizziness | 4 (2%) | 3 (2%) | 1 (2%)
Postoperative infection | 5 (2%) | 7 (4%) | 0
Hypoxia | 4 (2%) | 5 (3%) | 0
Apnea | 4 (2%) | 1 (< 1%) | 1 (2%)
Hypertension | 3 (1%) | 3 (2%) | 0
Shivering | 3 (1%) | 1 (< 1%) | 0
Heartburn | 3 (1%) | 3 (2%) | 0
Atrial flutter | 3 (1%) | 1 (< 1%) | 0
Arrhythmia | 3 (1%) | 5 (3%) | 0
Hallucinations | 3 (1%) | 3 (2%) | 0
Pneumonia | 3 (1%) | 3 (2%) | 1 (2%)
Pharyngitis | 3 (1%) | 1 (< 1%) | 1 (2%)
Decreased mental acuity | 3 (1%) | 1 (< 1%) | 0
Dyspnea | 3 (1%) | 1 (< 1%) | 0
Cough | 3 (1%) | 0 | 0
Decreased cardiac output | 1 (< 1%) | 0 | 3 (7%)
Renal insufficiency | 1 (< 1%) | 5 (3%) | 0
Bradycardia | 1 (< 1%) | 1 (< 1%) | 1 (2%)
Urine retention | 2 (< 1%) | 3 (2%) | 0
Cerebral infarction | 2 (< 1%) | 2 (1%) | 1 (2%)
Premature ventricular beats | 2 (< 1%) | 3 (2%) | 0
Cerebral ischemia | 1 (< 1%) | 1 (< 1%) | 1 (2%)
Paresthesia | 2 (< 1%) | 2 (1%) | 0
Seizure | 2 (< 1%) | 1 (< 1%) | 1 (2%)
Sleep disorder | 1 (< 1%) | 1 (< 1%) | 1 (2%)
Bronchospasm | 1 (< 1%) | 6 (3%) | 0
Atelectasis | 2 (< 1%) | 3 (2%) | 0
Respiratory depression | 2 (< 1%) | 3 (2%) | 0
Pulmonary edema | 1 (< 1%) | 2 (1%) | 0
Respiratory distress | 2 (< 1%) | 0 | 1 (2%)
Hyperkalemia | 2 (< 1%) | 3 (2%) | 0
Electrolyte disorder | 0 | 3 (2%) | 0
Chest congestion | 0 | 3 (2%) | 0
Hemoptysis | 0 | 2 (1%) | 0
Facial ptosis | 0 | 2 (1%) | 0
Hemorrhage | 0 | 2 (1%) | 0
Hematuria | 0 | 1 (< 1%) | 1 (2%)
Visual disturbance(s) | 0 | 1 (< 1%) | 1 (2%)
Hypokalemia | 0 | 2 (1%) | 0
Exacerbation of renal failure | 0 | 0 | 1 (2%)
Blood in stool | 0 | 0 | 1 (2%)
First degree heart block | 0 | 0 | 1 (2%)
Pericarditis | 0 | 0 | 1 (2%)

Pediatrics

ULTIVA has been studied in 342 pediatric patients in controlled clinical studies for maintenance of general anesthesia. In the pediatric population (birth to 12 years), the most commonly reported events were nausea, vomiting, and shivering.

The frequencies of adverse events during general anesthesia with the recommended doses of ULTIVA are given in Table 17. Each patient was counted once for each type of adverse event.

There were no adverse events ≥ 1% for any treatment group during the maintenance period in the pediatric patient general anesthesia studies.

Table 17: Adverse Events Reported in ≥ 1% of Pediatric Patients Receiving ULTIVA in General Anesthesia Studies at the Recommended Doses [See Table 2 for recommended doses.] of ULTIVA
 | Recovery |  |  | Follow-up [In subjects receiving halothane (n = 22), 10 (45%) experienced vomiting.]
Adverse Event | ULTIVA (n = 342) | Fentanyl (n = 103) | Bupivacaine (n = 86) | ULTIVA (n = 342) | Fentanyl (n = 103) | Bupivacaine (n = 86)
Vomiting | 40 (12%) | 9 (9%) | 10 (12%) | 56 (16%) | 8 (8%) | 12 (14%)
Nausea | 23 (8%) | 7 (7%) | 1 (1%) | 17 (6%) | 6 (6%) | 5 (6%)
Shivering | 9 (3%) | 0 | 0 | 0 | 0 | 0
Rhonchi | 8 (3%) | 2 (2%) | 0 | 0 | 0 | 0
Postoperative complication | 5 (2%) | 2 (2%) | 0 | 4 (1%) | 0 | 0
Stridor | 4 (1%) | 2 (2%) | 0 | 0 | 0 | 0
Cough | 4 (1%) | 1 (< 1%) | 0 | 0 | 0 | 0

6.2 Postmarketing Experience

The following adverse reactions have been identified during post approval use of remifentanil. Because these reactions are reported voluntarily from a population of uncertain size, it is not always possible to reliably estimate their frequency or establish a causal relationship to drug exposure.

Cardiovascular: Asystole

Serotonin Syndrome: Cases of serotonin syndrome, a potentially life-threatening condition, have been reported during concomitant use of opioids with serotonergic drugs.

Anaphylaxis: Anaphylaxis has been reported with ingredients contained in ULTIVA.

Hyperalgesia and Allodynia: Cases of hyperalgesia and allodynia have been reported with opioid therapy of any duration [see Warnings and Precautions (5.4)].

Hypoglycemia: Cases of hypoglycemia have been reported in patients taking opioids. Most reports were in patients with at least one predisposing risk factor (e.g., diabetes).

Opioid-Induced Esophageal Dysfunction (OIED): Cases of OIED have been reported in patients taking opioids and may occur more frequently in patients taking higher doses of opioids, and/or in patients taking opioids longer term.

7 DRUG INTERACTIONS

Table 18 includes clinically significant drug interactions with ULTIVA.

Table 18: Clinically Significant Drug Interactions with ULTIVA
Benzodiazepines and other Central Nervous System (CNS) Depressants
Clinical Impact: | Due to additive pharmacologic effect, the concomitant use of benzodiazepines or other CNS depressants including alcohol, increases the risk of hypotension, respiratory depression, profound sedation, coma, and death [see Warnings and Precautions (5.3)].
Intervention: | Limit dosages and durations to the minimum required. Follow patients closely for signs of respiratory depression and sedation. Patients should be advised to avoid alcohol for 24 hours after surgery [see Warnings and Precautions (5.3)].
Examples: | Benzodiazepines and other sedatives/hypnotics, anxiolytics, tranquilizers, muscle relaxants, general anesthetics, antipsychotics, gabapentinoids (gabapentin or pregabalin), other opioids, alcohol.
Serotonergic Drugs
Clinical Impact: | The concomitant use of opioids with other drugs that affect the serotonergic neurotransmitter system has resulted in serotonin syndrome [see Warnings and Precautions (5.5)].
Intervention: | If concomitant use is warranted, carefully observe the patient, particularly during treatment initiation and dose adjustment. Discontinue ULTIVA if serotonin syndrome is suspected.
Examples: | Selective serotonin reuptake inhibitors (SSRIs), serotonin and norepinephrine reuptake inhibitors (SNRIs), tricyclic antidepressants (TCAs), triptans, 5-HT3 receptor antagonists, drugs that effect the serotonin neurotransmitter system (e.g., mirtazapine, trazodone, tramadol), certain muscle relaxants (i.e., cyclobenzaprine, metaxalone), monoamine oxidase (MAO) inhibitors (those intended to treat psychiatric disorders and also others, such as linezolid and intravenous methylene blue).
Monoamine Oxidase Inhibitors (MAOIs)
Clinical Impact: | MAOI interactions with opioids may manifest as serotonin syndrome [see Warnings and Precautions (5.5)] or opioid toxicity (e.g., respiratory depression, coma) [see Warnings and Precautions (5.2)].; If urgent use of ULTIVA is necessary, use test doses and frequent titration of small doses while closely monitoring blood pressure and signs and symptoms of CNS and respiratory depression.
Intervention: | The use of ULTIVA is not recommended for patients taking MAOIs or within 14 days of stopping such treatment.
Mixed Agonist/Antagonist and Partial Agonist Opioid Analgesics
Clinical Impact: | May reduce the analgesic effect of ULTIVA and/or precipitate withdrawal symptoms.
Intervention: | If concomitant use is warranted, carefully observe the patient, particularly during treatment initiation and dose adjustment. Consider discontinuing ULTIVA if patient is not responding appropriately to treatment and institute alternative analgesic treatment.
Examples: | butorphanol, nalbuphine, pentazocine, buprenorphine

8 USE IN SPECIFIC POPULATIONS

8.1 Pregnancy

Risk Summary

Use of opioid analgesics for an extended period of time during pregnancy may cause neonatal opioid withdrawal syndrome. Available data with remifentanil hydrochloride in pregnant women are insufficient to inform a drug-associated risk for major birth defects and miscarriage. In animal reproduction studies, reduced fetal rat body weight and pup weights were reported at 2.2 times a human intravenous infusion of an induction dose of 1 mcg/kg with a maintenance dose of 2 mcg/kg/min for a surgical procedure lasting 3 hours. There were no malformations noted when remifentanil was administered via bolus injection to pregnant rats or rabbits during organogenesis at doses approximately 5 times and approximately equal, respectively, to a human intravenous infusion of an induction dose of 1 mcg/kg with a maintenance dose of 2 mcg/kg/min for a surgical procedure lasting 3 hours [see Data]. The estimated background risk of major birth defects and miscarriage for the indicated population is unknown. All pregnancies have a background risk of birth defect, loss, or other adverse outcomes. In the U.S. general population, the estimated background risk of major birth defects and miscarriage in clinically recognized pregnancies is 2-4% and 15-20%, respectively.

Clinical Considerations

Labor or Delivery

Opioids cross the placenta and may produce respiratory depression and psycho-physiologic effects in neonates. An opioid overdose reversal agent, such as naloxone or nalmefene, must be available for reversal of opioid-induced respiratory depression in the neonate. ULTIVA is not recommended for use in pregnant women during or immediately prior to labor, when other analgesic techniques are more appropriate. Opioid analgesics, including ULTIVA, can prolong labor through actions which temporarily reduce the strength, duration, and frequency of uterine contractions. However, this effect is not consistent and may be offset by an increased rate of cervical dilation, which tends to shorten labor. Monitor neonates exposed to opioid analgesics during labor for signs of excess sedation and respiratory depression.

Data

Human Data

In a human clinical trial, the average maternal remifentanil concentrations were approximately twice those seen in the fetus. In some cases, however, fetal concentrations were similar to those in the mother. The umbilical arteriovenous ratio of remifentanil concentrations was approximately 30% suggesting metabolism of remifentanil in the neonate.

Animal Data

Pregnant rats were treated from Gestation Day 6 to 15 with intravenous remifentanil doses of 0.5, 1.6, or 5 mg/kg/day (0.2, 0.7, or 2.2 times a human intravenous infusion of an induction dose of 1 mcg/kg with a maintenance dose of 2 mcg/kg/min based on body surface area for a surgical procedure lasting 3 hours based on body surface area, respectively). Reduced fetal weights were reported in the high dose group; however, no malformations were reported in surviving fetuses despite a non-dose dependent increase in maternal mortality.

Pregnant rabbits were treated from Gestation Day 6 to 18 with intravenous remifentanil doses of 0.1, 0.5, or 0.8 mg/kg/day (0.09, 0.4, or 0.7 times a human intravenous infusion of an induction dose of 1 mcg/kg with a maintenance dose of 2 mcg/kg/min based on body surface area for a surgical procedure lasting 3 hours based on body surface area, respectively). No malformations were reported in surviving fetuses despite clear maternal toxicity (decreased food consumption and body weights and increased mortality in all treatment groups).

Pregnant rats were treated from Gestation Day 6 to Lactation Day 21 with intravenous boluses of remifentanil 0.5, 1.6, or 5 mg/kg/day (0.2, 0.7, or 2.2 times a human intravenous infusion of an induction dose of 1 mcg/kg with a maintenance dose of 2 mcg/kg/min based on body surface area for a surgical procedure lasting 3 hours based on body surface area, respectively). Reduced birth weights were noted in the high-dose groups in the presence of maternal toxicity (increased mortality in all groups).

8.2 Lactation

Risk Summary

It is not known whether remifentanil is excreted in human milk. After receiving radioactive-labeled remifentanil, the radioactivity was present in the milk of lactating rats. Because fentanyl analogs are excreted in human milk, caution should be exercised when ULTIVA is administered to a nursing woman.

The developmental and health benefits of breastfeeding should be considered along with the mother’s clinical need for ULTIVA and any potential adverse effects on the breastfed infant from ULTIVA or from the underlying maternal condition.

Clinical Considerations

Infants exposed to ULTIVA through breast milk should be monitored for excess sedation and respiratory depression. Withdrawal symptoms can occur in breastfed infants when maternal administration of an opioid analgesic is stopped, or when breast-feeding is stopped.

8.4 Pediatric Use

The efficacy and safety of ULTIVA as an analgesic agent for use in the maintenance of general anesthesia in outpatient and inpatient pediatric surgery have been established in controlled clinical studies in pediatric patients from birth to 12 years [see Clinical Studies (14.4)].

The initial maintenance infusion regimen of ULTIVA evaluated in pediatric patients from birth to 2 months of age was 0.4 mcg/kg/min, the approved adult regimen for use with N2O. The clearance rate observed in neonates was highly variable and on average was 2 times higher than in the young healthy adult population. Therefore, while a starting infusion rate of 0.4 mcg/kg/min may be appropriate for some neonates, an increased infusion rate may be necessary to maintain adequate surgical anesthesia, and additional bolus doses may be required. The individual dose for each patient should be carefully titrated. [See Clinical Pharmacology: Specific Populations: Pediatric Population (12.3) and Dosage and Administration, Table 2 and Maintenance of Anesthesia (2.2).]

ULTIVA has not been studied in pediatric patients for use as a postoperative analgesic or as an analgesic component of monitored anesthesia care.

8.5 Geriatric Use

Respiratory depression is the chief risk for elderly patients treated with opioids and has occurred after large initial doses were administered to patients who were not opioid-tolerant or when opioids were co-administered with other agents that depress respiration. Titrate the dosage of ULTIVA slowly in geriatric patients and frequently reevaluate the patient for signs of central nervous system and respiratory depression [see Warnings and Precautions (5.2)].

Of the total number of subjects in clinical studies of ULTIVA, 486 were 65 and over (age range 66 to 90 years). While the effective biological half-life of remifentanil is unchanged, elderly patients have been shown to be twice as sensitive as the younger population to the pharmacodynamic effects of remifentanil. The recommended starting dose of ULTIVA should be decreased by 50% in patients over 65 years of age [see Clinical Pharmacology (12.3) and Dosage and Administration (2.2)]. Titrate the dosage of ULTIVA slowly in geriatric patients. [See Warnings and Precautions (5.5).]

The clearance of remifentanil is reduced (approximately 25%) in the elderly (> 65 years of age) compared to young adults (average 25 years of age). However, remifentanil blood concentrations fall as rapidly after termination of administration in the elderly as in young adults.

This drug is known to be substantially excreted by the kidney, and the risk of adverse reactions to this drug may be greater in patients with impaired renal function. Because elderly patients are more likely to have decreased renal function, care should be taken in dose selection, and it may be useful to monitor renal function.

8.6 Use in Morbidly Obese Patients

As for all potent opioids, caution is required with use in morbidly obese patients because of alterations in cardiovascular and respiratory physiology [see Dosage and Administration (2.2)].

8.7 Long-Term Use in the ICU

No data are available on the long-term (longer than 16 hours) use of ULTIVA as an analgesic in ICU patients.

9 DRUG ABUSE AND DEPENDENCE

9.1 Controlled Substance

ULTIVA contains remifentanil, a Schedule II controlled substance.

9.2 Abuse

ULTIVA contains remifentanil, a substance with high potential for misuse and abuse, which can lead to the development of substance use disorder, including addiction [see Warnings and Precautions (5.1)].

Misuse is the intentional use, for therapeutic purposes, of a drug by an individual in a way other than prescribed by a healthcare provider or for whom it was not prescribed.

Abuse is the intentional, non-therapeutic use of a drug, even once, for its desirable psychological or physiological effects.

Drug addiction is a cluster of behavioral, cognitive, and physiological phenomena that may include a strong desire to take the drug, difficulties in controlling drug use (e.g., continuing drug use despite harmful consequences, giving a higher priority to drug use than other activities and obligations), and possible tolerance or physical dependence.

Misuse and abuse of ULTIVA increases risk of overdosage, which may lead to central nervous system and respiratory depression, hypotension, seizures, and death. The risk is increased with concurrent abuse of ULTIVA with alcohol and/or other CNS depressants. Abuse of and addiction to opioids in some individuals may not be accompanied by concurrent tolerance and symptoms of physical dependence. In addition, abuse of opioids can occur in the absence of addiction.

All patients treated with opioids require careful and frequent reevaluation for signs of misuse, abuse, and addiction, because use of opioid analgesic products carries the risk of addiction even under appropriate medical use. Patients at high risk of ULTIVA abuse include those with a history of prolonged use of any opioid, including products containing remifentanil, those with a history of drug or alcohol abuse, or those who use ULTIVA in combination with other abused drugs.

“Drug-seeking” behavior is very common in persons with substance use disorders. Drug-seeking tactics include emergency calls or visits near the end of office hours, refusal to undergo appropriate examination, testing, or referral, repeated “loss” of prescriptions, tampering with prescriptions, and reluctance to provide prior medical records or contact information for other treating healthcare provider(s). “Doctor shopping” (visiting multiple prescribers to obtain additional prescriptions) is common among people who abuse drugs and people with substance use disorder. Preoccupation with achieving adequate pain relief can be appropriate behavior in a patient with inadequate pain control.

ULTIVA, like other opioids, can be diverted for nonmedical use into illicit channels of distribution. Careful record-keeping of prescribing information, including quantity, frequency, and renewal requests, as required by state and federal law, is strongly advised.

Proper assessment of the patient, proper prescribing practices, periodic reevaluation of therapy, and proper dispensing and storage are appropriate measures that help to limit abuse of opioid drugs.

Risks Specific to Abuse of ULTIVA

Abuse of ULTIVA poses a risk of overdose and death. The risk is increased with concurrent use of ULTIVA with alcohol and/or other CNS depressants.

Parenteral drug abuse is commonly associated with transmission of infectious diseases such as hepatitis and HIV.

9.3 Dependence

Both tolerance and physical dependence can develop during use of opioid therapy.

Tolerance is a physiological state characterized by a reduced response to a drug after repeated administration (i.e., a higher dose of a drug is required to produce the same effect that was once obtained at a lower dose).

Physical dependence is a state that develops as a result of a physiological adaptation in response to repeated drug use, manifested by withdrawal signs and symptoms after abrupt discontinuation or a significant dosage reduction of a drug.

Withdrawal may be precipitated through the administration of drugs with opioid antagonist activity (e.g., naloxone, nalmefene), mixed agonist/antagonist analgesics (e.g., pentazocine, butorphanol, nalbuphine), or partial agonists (e.g., buprenorphine). Physical dependence may not occur to a clinically significant degree until after several days to weeks of continued use.

ULTIVA should not be rapidly reduced or abruptly discontinued in a physically-dependent patient [see Dosage and Administration (2)]. If ULTIVA is rapidly reduced or abruptly discontinued in a physically-dependent patient, a withdrawal syndrome may occur, typically characterized by restlessness, lacrimation, rhinorrhea, perspiration, chills, myalgia, and mydriasis. Other signs and symptoms also may develop, including irritability, anxiety, backache, joint pain, weakness, abdominal cramps, insomnia, nausea, anorexia, vomiting, diarrhea, or increased blood pressure, respiratory rate, or heart rate.

Infants born to mothers physically dependent on opioids will also be physically dependent and may exhibit respiratory difficulties and withdrawal signs [see Use in Specific Populations (8.1)].

10 OVERDOSAGE

Clinical Presentation

Acute overdose with remifentanil can be manifested by respiratory depression, somnolence progressing to stupor or coma, skeletal muscle flaccidity, cold and clammy skin, constricted pupils, and, in some cases, pulmonary edema, bradycardia, hypotension, hypoglycemia, partial or complete airway obstruction, atypical snoring, and death. Marked mydriasis rather than miosis may be seen with hypoxia in overdose situations [see Clinical Pharmacology (12.2)]. Toxic leukoencephalopathy has been reported after opioid overdose and can present hours, days, or weeks after apparent recovery from the initial intoxication.

Treatment of Overdose

In case of overdose, priorities are the reestablishment of a patent and protected airway and institution of assisted or controlled ventilation, if needed. Employ other supportive measures (including oxygen and vasopressors) in the management of circulatory shock and pulmonary edema as indicated. Cardiac arrest or arrhythmias will require advanced life-support measures.

For clinically significant respiratory or circulatory depression secondary to remifentanil overdose, stop the infusion or administer an opioid overdose reversal agent such as naloxone or nalmefene. Opioid overdose reversal agents should not be administered in the absence of clinically significant respiratory or circulatory depression secondary to remifentanil overdose.

In an individual physically dependent on opioids, administration of the recommended usual dosage of the opioid overdose reversal agent will precipitate an acute withdrawal syndrome. The severity of the withdrawal symptoms experienced will depend on the degree of physical dependence and the dose of the reversal agent administered. If a decision is made to treat serious respiratory depression in the physically dependent patient, administration of the reversal agent should be begun with care and by titration with smaller than usual doses of the reversal agent.

11 DESCRIPTION

ULTIVA (remifentanil hydrochloride) for injection is an opioid agonist. The chemical name is 3-[4-methoxycarbonyl-4-[(1-oxopropyl)phenylamino]-1-piperidine]propanoic acid methyl ester, hydrochloride salt. The molecular weight is 412.91. Its molecular formula is C20H28N2O5•HCl, and it has the following chemical structure.

ULTIVA is a sterile, nonpyrogenic, preservative-free, white to off-white lyophilized powder for intravenous (IV) administration after reconstitution and dilution. Each vial contains 1 mg, 2 mg, or 5 mg of remifentanil base; 15 mg glycine; and hydrochloric acid to buffer the solutions to a nominal pH of 3 after reconstitution. When reconstituted as directed, solutions of ULTIVA are clear and colorless and contain remifentanil hydrochloride (HCl) equivalent to 1 mg/mL of remifentanil base. The pH of reconstituted solutions of ULTIVA ranges from 2.5 to 3.5. Remifentanil hydrochloride has a pKa of 7.07. Remifentanil hydrochloride has an n-octanol:water partition coefficient of 17.9 at pH 7.3.

12 CLINICAL PHARMACOLOGY

12.1 Mechanism of Action

ULTIVA is a µ-opioid agonist with rapid onset and peak effect, and short duration of action. The µ-opioid activity of ULTIVA is antagonized by opioid antagonists, including overdose reversal agents such as naloxone or nalmefene.

Unlike other opioids, ULTIVA is rapidly metabolized by hydrolysis of the propanoic acid-methyl ester linkage by nonspecific blood and tissue esterases. ULTIVA is not a substrate for plasma cholinesterase (pseudocholinesterase) and, therefore, patients with atypical cholinesterase are expected to have a normal duration of action.

12.2 Pharmacodynamics

The analgesic effects of ULTIVA are rapid in onset and offset. Its effects and side effects are dose dependent and similar to other µ-opioids. ULTIVA in humans has a rapid blood-brain equilibration half-time of 1 ± 1 minutes (mean ± SD) and a rapid onset of action. The pharmacodynamic effects of ULTIVA closely follow the measured blood concentrations, allowing direct correlation between dose, blood levels, and response. Blood concentration decreases 50% in 3 to 6 minutes after a 1-minute infusion or after prolonged continuous infusion due to rapid distribution and elimination processes and is independent of duration of drug administration. Recovery from the effects of ULTIVA occurs rapidly (within 5 to 10 minutes). New steady-state concentrations occur within 5 to 10 minutes after changes in infusion rate. When used as a component of an anesthetic technique, ULTIVA can be rapidly titrated to the desired depth of anesthesia/analgesia (e.g., as required by varying levels of intraoperative stress) by changing the continuous infusion rate or by administering an IV bolus injection.

Effects on the Central Nervous System

Remifentanil produces respiratory depression by direct action on brain stem respiratory centers. The respiratory depression involves both a reduction in the responsiveness of the brain stem respiratory centers to increases in carbon dioxide tension and to electrical stimulation.

Remifentanil causes miosis, even in total darkness. Pinpoint pupils are a sign of opioid overdose but are not pathognomonic (e.g., pontine lesions of hemorrhagic or ischemic origins may produce similar findings). Marked mydriasis rather than miosis may be seen due to hypoxia in overdose situations.

Effects on the Gastrointestinal Tract and Other Smooth Muscle

Remifentanil causes a reduction in motility associated with an increase in smooth muscle tone in the antrum of the stomach and duodenum. Digestion of food in the small intestine is delayed and propulsive contractions are decreased. Propulsive peristaltic waves in the colon are decreased, while tone may be increased to the point of spasm resulting in constipation. Other opioid-induced effects may include a reduction in biliary and pancreatic secretions, spasm of sphincter of Oddi, transient elevations in serum amylase, and opioid-induced esophageal dysfunction (OIED).

Effects on the Cardiovascular System

Remifentanil produces peripheral vasodilation which may result in orthostatic hypotension or syncope. Manifestations of histamine release and/or peripheral vasodilation may include pruritus, flushing, red eyes and sweating and/or orthostatic hypotension. Caution must be used in hypovolemic patients, such as those suffering acute myocardial infarction, because remifentanil may cause or further aggravate their hypotension. Caution must also be used in patients with cor pulmonale who have received therapeutic doses of opioids.

Effects on the Endocrine System

Opioids inhibit the secretion of adrenocorticotropic hormone (ACTH), cortisol, and luteinizing hormone (LH) in humans. They also stimulate prolactin, growth hormone (GH) secretion, and pancreatic secretion of insulin and glucagon.

Effects on the Immune System

Opioids have been shown to have a variety of effects on components of the immune system in in vitro and animal models. The clinical significance of these findings is unknown. Overall, the effects of opioids appear to be modestly immunosuppressive.

Concentration–Efficacy Relationships

The minimum effective analgesic concentration will vary widely among patients, especially among patients who have been previously treated with opioid agonists [see Dosage and Administration (2.1, 2.2)]. The minimum effective analgesic concentration of remifentanil for any individual patient may increase over time due to an increase in pain, the development of a new pain syndrome and/or the development of analgesic tolerance.

Concentration–Adverse Reaction Relationships

There is a relationship between increasing remifentanil plasma concentration and increasing frequency of dose-related opioid adverse reactions such as nausea, vomiting, CNS effects, and respiratory depression. In opioid-tolerant patients, the situation may be altered by the development of tolerance to opioid-related adverse reactions [see Dosage and Administration (2.1, 2.2)].

Hemodynamics

In premedicated patients undergoing anesthesia, 1-minute infusions of < 2 mcg/kg of ULTIVA cause dose-dependent hypotension and bradycardia. While additional doses > 2 mcg/kg (up to 30 mcg/kg) do not produce any further decreases in heart rate or blood pressure, the duration of the hemodynamic change is increased in proportion to the blood concentrations achieved. Peak hemodynamic effects occur within 3 to 5 minutes of a single dose of ULTIVA or an infusion rate increase. Glycopyrrolate, atropine, and vagolytic neuromuscular blocking agents attenuate the hemodynamic effects associated with ULTIVA. When appropriate, bradycardia and hypotension can be reversed by reduction of the rate of infusion of ULTIVA, or the dose of concurrent anesthetics, or by the administration of fluids or vasopressors.

Respiration

ULTIVA depresses respiration in a dose-related fashion. Unlike other fentanyl analogs, the duration of action of ULTIVA at a given dose does not increase with increasing duration of administration, due to lack of drug accumulation. When ULTIVA and alfentanil were dosed to equal levels of respiratory depression, recovery of respiratory drive after 3-hour infusions was more rapid and less variable with ULTIVA (see Figure 1).

Figure 1: Recovery of Respiratory Drive After Equipotent* Doses of ULTIVA and Alfentanil Using CO2-Stimulated Minute Ventilation in Adult Volunteers (±1.5 SEM)

Spontaneous respiration occurs at blood concentrations of 4 to 5 ng/mL in the absence of other anesthetic agents; for example, after discontinuation of a 0.25 mcg/kg/min infusion of remifentanil, these blood concentrations would be reached in 2 to 4 minutes. In patients undergoing general anesthesia, the rate of respiratory recovery depends upon the concurrent anesthetic; N2O < propofol < isoflurane [see Clinical Studies: Recovery (14.2)].

Muscle Rigidity

Skeletal muscle rigidity can be caused by ULTIVA and is related to the dose and speed of administration. ULTIVA may cause chest wall rigidity (inability to ventilate) after single doses of > 1 mcg/kg administered over 30 to 60 seconds or infusion rates > 0.1 mcg/kg/min; peripheral muscle rigidity may occur at lower doses. Administration of doses < 1 mcg/kg may cause chest wall rigidity when given concurrently with a continuous infusion of ULTIVA.

Histamine Release

Assays of histamine in patients and normal volunteers have shown no elevation in plasma histamine levels after administration of ULTIVA in doses up to 30 mcg/kg over 60 seconds.

Analgesia

Infusions of 0.05 to 0.1 mcg/kg/min, producing blood concentrations of 1 to 3 ng/mL, are typically associated with analgesia with minimal decrease in respiratory rate. Supplemental doses of 0.5 to 1 mcg/kg, incremental increases in infusion rate > 0.05 mcg/kg/min, and blood concentrations exceeding 5 ng/mL (typically produced by infusions of 0.2 mcg/kg/min) have been associated with transient and reversible respiratory depression, apnea, and muscle rigidity.

Anesthesia

ULTIVA is synergistic with the activity of hypnotics (propofol and thiopental), inhaled anesthetics, and benzodiazepines [see Clinical Studies (14.1), Warnings and Precautions (5), and Dosage and Administration (2)].

Age

The pharmacodynamic activity of ULTIVA (as measured by the EC50 for development of delta waves on the EEG) increases with increasing age. The EC50 of remifentanil for this measure was 50% less in patients over 65 years of age when compared to healthy volunteers (25 years of age) [see Dosage and Administration (2.2)].

Sex

No differences have been shown in the pharmacodynamic activity (as measured by the EEG) of ULTIVA between men and women.

Drug Interactions

In animals the duration of muscle paralysis from succinylcholine is not prolonged by remifentanil.

Intraocular Pressure

There was no change in intraocular pressure after the administration of ULTIVA prior to ophthalmic surgery under monitored anesthesia care.

Cerebrodynamics

Under isoflurane-nitrous oxide anesthesia (PaCO2 < 30 mmHg), a 1-minute infusion of ULTIVA (0.5 or 1.0 mcg/kg) produced no change in intracranial pressure. Mean arterial pressure and cerebral perfusion decreased as expected with opioids. In patients receiving ULTIVA and nitrous oxide anesthesia, cerebrovascular reactivity to carbon dioxide remained intact. In humans, no epileptiform activity was seen on the EEG (n = 44) at remifentanil doses up to 8 mcg/kg/min.

Renal Dysfunction

The pharmacodynamics of ULTIVA (ventilatory response to hypercarbia) are unaltered in patients with end stage renal disease (creatinine clearance < 10 mL/min).

Hepatic Dysfunction

The pharmacodynamics of ULTIVA (ventilatory response to hypercarbia) are unaltered in patients with severe hepatic dysfunction awaiting liver transplant.

12.3 Pharmacokinetics

After IV doses administered over 60 seconds, the pharmacokinetics of remifentanil fit a three-compartment model with a rapid distribution half-life of one minute, a slower distribution half-life of 6 minutes, and a terminal elimination half-life of 10 to 20 minutes. Since the terminal elimination component contributes less than 10% of the overall area under the concentration versus time curve (AUC), the effective biological half-life of ULTIVA is 3 to 10 minutes. This is similar to the 3- to 10-minute half-life measured after termination of prolonged infusions (up to 4 hours; see Figure 2) and correlates with recovery times observed in the clinical setting after infusions up to 12 hours. Concentrations of remifentanil are proportional to the dose administered throughout the recommended dose range. The pharmacokinetics of remifentanil are unaffected by the presence of renal or hepatic impairment.

Distribution

The initial volume of distribution (Vd) of remifentanil is approximately 100 mL/kg and represents distribution throughout the blood and rapidly perfused tissues. Remifentanil subsequently distributes into peripheral tissues with a steady-state volume of distribution of approximately 350 mL/kg. These two distribution volumes generally correlate with total body weight (except in severely obese patients when they correlate better with ideal body weight [IBW]). Remifentanil is approximately 70% bound to plasma proteins of which two-thirds is binding to alpha-1-acid-glycoprotein.

Elimination

The clearance of remifentanil in young, healthy adults is approximately 40 mL/min/kg. Clearance generally correlates with total body weight (except in severely obese patients when it correlates better with IBW). The high clearance of remifentanil combined with a relatively small volume of distribution produces a short elimination half-life of approximately 3 to 10 minutes (see Figure 2). This value is consistent with the time taken for blood or effect site concentrations to fall by 50% (context-sensitive half-times) which is approximately 3 to 6 minutes. Unlike other fentanyl analogs, the duration of action does not increase with prolonged administration.

Figure 2: Mean Concentration (sd) versus Time

Titration to Effect

The rapid elimination of remifentanil permits the titration of infusion rate without concern for prolonged duration. In general, every 0.1 mcg/kg/min change in the IV infusion rate will lead to a corresponding 2.5 ng/mL change in blood remifentanil concentration within 5 to 10 minutes. In intubated patients only, a more rapid increase (within 3 to 5 minutes) to a new steady state can be achieved with a 1.0 mcg/kg bolus dose in conjunction with an infusion rate increase.

Metabolism

Remifentanil is an esterase-metabolized opioid. A labile ester linkage renders this compound susceptible to hydrolysis by nonspecific esterases in blood and tissues. This hydrolysis results in the production of the carboxylic acid metabolite (3-[4-methoxycarbonyl-4-[(1-oxopropyl)phenylamino]-1-piperidine]propanoic acid), and represents the principal metabolic pathway for remifentanil (> 95%). The carboxylic acid metabolite is essentially inactive (1/4600 as potent as remifentanil in dogs). Remifentanil is not metabolized by plasma cholinesterase (pseudocholinesterase) and is not appreciably metabolized by the liver or lung.

Excretion

The carboxylic acid metabolite is excreted by the kidneys with an elimination half-life of approximately 90 minutes.

Specific Populations

Age: Geriatric Population

The clearance of remifentanil is reduced (approximately 25%) in the elderly (> 65 years of age) compared to young adults (average 25 years of age). However, remifentanil blood concentrations fall as rapidly after termination of administration in the elderly as in young adults.

Age: Pediatric Population

In pediatric patients, 5 days to 17 years of age (n = 47), the clearance and volume of distribution of remifentanil were increased in younger children and declined to young healthy adult values by age 17. The average clearance of remifentanil in neonates (less than 2 months of age) was approximately 90.5 ± 36.8 mL/min/kg (mean ± SD) while in adolescents (13 to 16 years) this value was 57.2 ± 21.1 mL/min/kg. The total (steady-state) volume of distribution in neonates was 452 ± 144 mL/kg versus 223 ± 30.6 mL/kg in adolescents. The half-life of remifentanil was the same in neonates and adolescents. Clearance of remifentanil was maintained at or above normal adult values in patients 5 days to 17 years of age.

Sex

There is no significant difference in the pharmacokinetics of remifentanil in male and female patients after correcting for differences in weight.

Hepatic Impairment

The pharmacokinetics of remifentanil and its carboxylic acid metabolite are unchanged in patients with severe hepatic impairment.

Renal Impairment

The pharmacokinetic profile of ULTIVA is not changed in patients with end stage renal disease (creatinine clearance < 10 mL/min). In anephric patients, the half-life of the carboxylic acid metabolite increases from 90 minutes to 30 hours. The metabolite is removed by hemodialysis with a dialysis extraction ratio of approximately 30%.

Obesity

There is no difference in the pharmacokinetics of remifentanil in non-obese versus obese (greater than 30% over IBW) patients when normalized to IBW.

Cardiopulmonary Bypass (CPB)

Remifentanil clearance is reduced by approximately 20% during hypothermic CPB.

Drug Interaction Studies

Remifentanil clearance is not altered by concomitant administration of thiopental, isoflurane, propofol, or temazepam during anesthesia. In vitro studies with atracurium, mivacurium, esmolol, echothiophate, neostigmine, physostigmine, and midazolam revealed no inhibition of remifentanil hydrolysis in whole human blood by these drugs.

13 NONCLINICAL TOXICOLOGY

13.1 Carcinogenesis, Mutagenesis, Impairment of Fertility

Carcinogenesis

Long-term studies in animals to evaluate the carcinogenic potential of remifentanil have not been conducted.

Mutagenesis

Mutagenicity was observed with remifentanil in the in vitro mouse lymphoma assay in the presence but not

absence of metabolic activation. Remifentanil did not induce gene mutation in the in vitro bacterial reverse mutation assay (Ames test) and was not genotoxic in the in vivo rat hepatocyte unscheduled DNA synthesis assay. No clastogenic effect was seen in cultured Chinese hamster ovary cells or in the in vivo mouse micronucleus test.

Impairment of Fertility

Remifentanil has been shown to reduce fertility in male rats when tested after 70+ days of daily IV administration of 0.5 mg/kg, which is approximately 0.2 times a human intravenous infusion of an induction dose of 1 mcg/kg with a maintenance dose of 2 mcg/kg/min in terms of mg/m^2 of body surface area for a surgical procedure lasting 3 hours or 40 times a single bolus human dose of 2 mcg/kg, in terms of mg/m^2 of body surface area.

The fertility of female rats was not affected at IV doses as high as 1 mg/kg which is 0.4 times a human intravenous infusion of an induction dose of 1 mcg/kg with a maintenance dose of 2 mcg/kg/min in terms of mg/m^2 of body surface area for a surgical procedure lasting 3 hours or approximately 80 times a single bolus human dose of 2 mcg/kg, in terms of mg/m^2 of body surface area, when administered for at least 15 days before mating.

14 CLINICAL STUDIES

ULTIVA was evaluated in 3,341 patients undergoing general anesthesia (n = 2,706) and monitored anesthesia care (n = 639). These patients were evaluated in the following settings: inpatient (n = 2,079) which included cardiovascular (n = 426), and neurosurgical (n = 61), and outpatient (n = 1,349). Four-hundred and eighty-six (486) elderly patients (age range 66 to 90 years) and 410 pediatric patients (age range birth to 12 years) received ULTIVA. Of the general anesthesia patients, 682 also received ULTIVA as an IV analgesic agent during the immediate postoperative period.

14.1 Induction and Maintenance of General Anesthesia - Inpatient/Outpatient

The efficacy of ULTIVA was investigated in 1,562 patients in 15 randomized, controlled trials as the analgesic component for the induction and maintenance of general anesthesia. Eight of these studies compared ULTIVA to alfentanil and two studies compared ULTIVA to fentanyl. In these studies, doses of ULTIVA up to the ED90 were compared to recommended doses (approximately ED50) of alfentanil or fentanyl.

Induction of Anesthesia

ULTIVA was administered with isoflurane, propofol, or thiopental for the induction of anesthesia (n = 1,562). The majority of patients (80%) received propofol as the concurrent agent. ULTIVA reduced the propofol and thiopental requirements for loss of consciousness. Compared to alfentanil and fentanyl, a higher relative dose of ULTIVA resulted in fewer responses to intubation (see Table 19). Overall, hypotension occurred in 5% of patients receiving ULTIVA compared to 2% of patients receiving the other opioids.

ULTIVA has been used as a primary agent for the induction of anesthesia; however, it should not be used as a sole agent because loss of consciousness cannot be assured and because of a high incidence of apnea, muscle rigidity, and tachycardia. The administration of an induction dose of propofol or thiopental or a paralyzing dose of a muscle relaxant prior to or concurrently with ULTIVA during the induction of anesthesia markedly decreased the incidence of muscle rigidity from 20% to < 1%.

Table 19: Response to Intubation (Propofol/Opioid Induction [Propofol was titrated to loss of consciousness. Not all doses of ULTIVA were equipotent to the comparator opioid.])
Opioid Treatment Group/ (No. of Patients) | Initial Dose (mcg/kg) | Pre-Intubation Infusion Rate (mcg/kg/min) | No. (%) Muscle Rigidity | No. (%) Hypotension During Induction | No. (%) Response to Intubation
Study 1:
ULTIVA (35) | 1 | 0.1 | 1 (3%) | 0 | 27 (77%)
ULTIVA (35) | 1 | 0.4 | 3 (9%) | 0 | 11 (31%) [Differences were statistically significant (P < 0.02).]
Alfentanil (35) | 20 | 1.0 | 2 (6%) | 0 | 26 (74%)
Study 2:
ULTIVA (116) | 1 | 0.5 | 9 (8%) | 5 (4%) | 17 (15%)
Alfentanil (118) | 25 | 1.0 | 6 (5%) | 5 (4%) | 33 (28%)
Study 3:
ULTIVA (134) | 1 | 0.5 | 2 (1%) | 4 (3%) | 25 (19%)
Alfentanil (66) | 20 | 2.0 | 0 | 0 | 19 (29%)
Study 4:
ULTIVA (98) | 1 | 0.2 | 11 (11%) | 2 (2%) | 35 (36%)
ULTIVA (91) | 2 [Initial doses greater than 1 mcg/kg are not recommended.] | 0.4 | 11 (12%) | 2 (2%) | 12 (13%)
Fentanyl (97) | 3 | NA | 1 (1%) | 1 (1%) | 29 (30%)

Use During Maintenance of Anesthesia

ULTIVA was investigated in 929 patients in seven well controlled general surgery studies in conjunction with nitrous oxide, isoflurane, or propofol in both inpatient and outpatient settings. These studies demonstrated that ULTIVA could be dosed to high levels of opioid effect and rapidly titrated to optimize analgesia intraoperatively without delaying or prolonging recovery.

Compared to alfentanil and fentanyl, these higher relative doses (ED90) of ULTIVA resulted in fewer responses to intraoperative stimuli (see Table 20) and a higher frequency of hypotension (16% compared to 5% for the other opioids). ULTIVA was infused to the end of surgery, while alfentanil was discontinued 5 to 30 minutes before the end of surgery as recommended. The mean final infusion rates of ULTIVA were between 0.25 and 0.48 mcg/kg/min.

Table 20: Intraoperative Responses [Not all doses of ULTIVA were equipotent to the comparator opioid.]
Opioid Treatment Group/(No. of Patients) | Concurrent Anesthetic | Post-Intubation Infusion Rate (mcg/kg/min) | No. (%) With Intraoperative Hypotension | No. (%) With Response to Skin Incision | No. (%) With Signs of Light Anesthesia | No. (%) With Response to Skin Closure
Study 1:
ULTIVA (35) |  | 0.1 | 0 | 20 (57%) | 33 (94%) | 6 (17%)
ULTIVA (35) | Nitrous oxide | 0.4 | 0 | 3 (9%) [Differences were statistically significant (P < 0.05).] | 12 (34%) | 2 (6%)
Alfentanil (35) |  | 1.0 | 0 | 24 (69%) | 33 (94%) | 12 (34%)
Study 2:
ULTIVA (116) | Isoflurane + | 0.25 | 35 (30%) | 9 (8%) | 66 (57%) | 19 (16%)
Alfentanil (118) | Nitrous oxide | 0.5 | 12 (10%) | 20 (17%) | 85 (72%) | 25 (21%)
Study 3:
ULTIVA (134) | Propofol | 0.5 | 3 (2%) | 14 (11%) | 70 (52%) | 25 (19%)
Alfentanil (66) |  | 2.0 | 2 (3%) | 21 (32%) | 47 (71%) | 13 (20%)
Study 4:
ULTIVA (98) |  | 0.2 | 13 (13%) | 12 (12%) | 67 (68%) | 7 (7%)
ULTIVA (91) | Isoflurane | 0.4 | 16 (18%) | 4 (4%) | 44 (48%) | 3 (3%)
Fentanyl (97) |  | 1.5-3 mcg/kg prn | 7 (7%) | 32 (33%) | 84 (87%) | 11 (11%)

In three randomized, controlled studies (n = 407) during general anesthesia, ULTIVA attenuated the signs of light anesthesia within a median time of 3 to 6 minutes after bolus doses of 1 mcg/kg with or without infusion rate increases of 50% to 100% (up to a maximum rate of 2 mcg/kg/min).

In an additional double-blind, randomized study (n = 103), a constant rate (0.25 mcg/kg/min) of ULTIVA was compared to doubling the rate to 0.5 mcg/kg/min approximately 5 minutes before the start of the major surgical stress event. Doubling the rate decreased the incidence of signs of light anesthesia from 67% to 8% in patients undergoing abdominal hysterectomy, and from 19% to 10% in patients undergoing radical prostatectomy. In patients undergoing laminectomy the lower dose was adequate.

14.2 Recovery

In 2,169 patients receiving ULTIVA for periods up to 16 hours, recovery from anesthesia was rapid, predictable, and independent of the duration of the infusion of ULTIVA. In the seven controlled, general surgery studies, extubation occurred in a median of 5 minutes (range: -3 to 17 minutes in 95% of patients) in outpatient anesthesia and 10 minutes (range: 0 to 32 minutes in 95% of patients) in inpatient anesthesia. Recovery in studies using nitrous oxide or propofol was faster than in those using isoflurane as the concurrent anesthetic. There was no case of remifentanil-induced delayed respiratory depression occurring more than 30 minutes after discontinuation of remifentanil [see Warnings and Precautions (5.14)].

In a double-blind, randomized study, administration of morphine sulfate (0.15 mg/kg) intravenously 20 minutes before the anticipated end of surgery to 98 patients did not delay recovery of respiratory drive in patients undergoing major surgery with remifentanil-propofol total IV anesthesia.

14.3 Spontaneous Ventilation Anesthesia

Two randomized, dose-ranging studies (n = 127) examined the administration of ULTIVA to outpatients undergoing general anesthesia with a laryngeal mask. Starting infusion rates of ULTIVA of ≤ 0.05 mcg/kg/min provided supplemental analgesia while allowing spontaneous ventilation with propofol or isoflurane. Bolus doses of ULTIVA during spontaneous ventilation lead to transient periods of apnea, respiratory depression, and muscle rigidity.

14.4 Pediatric Anesthesia

ULTIVA has been evaluated for maintenance of general anesthesia in 410 pediatric patients from birth to 12 years undergoing inpatient and outpatient procedures. Four clinical studies have been performed.

Study 1, an open-label, randomized, controlled clinical trial (n = 129), compared ULTIVA (n = 68) with alfentanil (n = 19), isoflurane (n = 22), or propofol (n = 20) in children 2 to 12 years of age undergoing strabismus surgery. After induction of anesthesia which included the administration of atropine, ULTIVA was administered as an initial infusion of 1 mcg/kg/min with 70% nitrous oxide. The infusion rate required during maintenance of anesthesia was 0.73 to 1.95 mcg/kg/min. Time to extubation and to purposeful movement was a median of 10 minutes (range 1 to 24 minutes).

Study 2, a double-blind, randomized, controlled trial (n = 222), compared ULTIVA (n = 119) to fentanyl (n = 103) in children 2 to 12 years of age undergoing tonsillectomy with or without adenoidectomy. After induction of anesthesia, patients received a 0.25 mcg/kg/min infusion of ULTIVA or fentanyl by IV bolus with nitrous oxide/oxygen (2:1) and either halothane or sevoflurane for maintenance of anesthesia. The mean infusion rate required during maintenance of anesthesia was 0.3 mcg/kg/min (range 0.2 to 1.3 mcg/kg/min). The continuous infusion rate was decreased to 0.05 mcg/kg/min approximately 10 minutes prior to the end of surgery. Time to spontaneous purposeful movement was a median of 8 minutes (range 1 to 19 minutes). Time to extubation was a median of 9 minutes (range 2 to 19 minutes).

Study 3, an open-label, randomized, controlled trial (n = 271), compared ULTIVA (n = 185) with a regional anesthetic technique (n = 86) in children 1 to 12 years of age undergoing major abdominal, urological, or orthopedic surgery. Patients received a 0.25 mcg/kg/min infusion of ULTIVA following a 1.0 mcg/kg bolus or bupivacaine by epidural infusion, along with isoflurane and nitrous oxide after the induction of anesthesia. The mean infusion rate required during maintenance of anesthesia was 0.25 mcg/kg/min (range 0 to 0.75 mcg/kg/min). Both treatments were effective in attenuating responses to skin incision during surgery. The hemodynamic profile of the ULTIVA group was consistent with an opioid-based general anesthetic technique. Time to spontaneous purposeful movement was a median of 15 minutes (range, 2 to 75 minutes) in the remifentanil group. Time to extubation was a median of 13 minutes (range, 4 to 31 minutes) in the remifentanil group.

Study 4, an open-label, randomized, controlled trial (n = 60), compared ULTIVA (n = 38) with halothane (n = 22) in ASA 1 or 2, full term neonates and infants ≤ 8 weeks of age weighing at least 2500 grams who were undergoing pyloromyotomy. After induction of anesthesia, which included the administration of atropine, patients received 0.4 mcg/kg/min of ULTIVA or 0.4% halothane with 70% nitrous oxide for initial maintenance of anesthesia and then both agents were adjusted according to clinical response. Bolus doses of 1 mcg/kg administered over 30 to 60 seconds were used to treat brief episodes of hypertension and tachycardia, and infusion rates were increased by 50% to treat sustained hypertension and tachycardia. The range of infusion rates of ULTIVA required during maintenance of anesthesia was 0.4 to 1 mcg/kg/min.

Seventy-one percent (71%) of ULTIVA patients required supplementary boluses or rate increases from the starting dose of 0.4 mcg/kg/min to treat hypertension, tachycardia, movement or somatic signs of light anesthesia. Twenty-four percent of the patients required an increase from the initial rate of 0.4 mcg/kg/min prior to incision and 26% of patients required an infusion rate between 0.8 and 1.0 mcg/kg/min, most often during gastric manipulation. The continuous infusion rate was decreased to 0.05 mcg/kg/min approximately 10 minutes before the end of surgery.

In the ULTIVA group, median time from discontinuation of anesthesia to spontaneous purposeful movement was 6.5 minutes (range, 1 to 13 minutes) and median time to extubation was 8.5 minutes (range, 1 to 14 minutes).

The initial maintenance infusion regimen of ULTIVA evaluated in pediatric patients from birth to 2 months of age was 0.4 mcg/kg/min, the approved adult regimen for use with N2O. The clearance rate observed in the neonatal population was highly variable and on average was two times higher than in the young healthy adult population. [See Clinical Pharmacology: Specific Populations: Pediatric Population (12.3) and Dosage and Administration, Table 2 (2.2).]

No pediatric patients receiving ULTIVA required naloxone during the immediate postoperative recovery period.

14.5 Coronary Artery Bypass Surgery

ULTIVA was originally administered to 225 subjects undergoing elective CABG surgery in two dose-ranging studies without active comparators. Subsequently, two double-blind, double-dummy clinical studies (N = 426) evaluated ULTIVA (n = 236) at recommended doses versus active comparators (n = 190).

The first comparator study, a multi-center, randomized, double-blind, double-dummy, parallel-group study (N = 369), compared ULTIVA (n = 201) with fentanyl (n = 168) in adult patients undergoing elective CABG surgery. Subjects received 1 to 3 mg midazolam and 0.05 mg/kg morphine IV as premedication. Anesthesia was induced with propofol 0.5 mg/kg (higher doses administered with ULTIVA were associated with excessive hypotension) over one minute plus 10-mg boluses every 10 seconds until loss of consciousness followed by either cisatracurium 0.2 mg/kg or vecuronium 0.15 mg/kg. Patients randomized to ULTIVA received a 1 mcg/kg/min infusion of ULTIVA followed by a placebo bolus administered over 3 minutes. In the active control group, a placebo IV infusion was started and a fentanyl bolus 10 mcg/kg was administered over 3 minutes. All subjects received isoflurane titrated initially to end tidal concentration of 0.5%. During maintenance, the group randomized to ULTIVA received as needed 0.5-1 mcg/kg/min IV rate increases (to a maximum of 4 mcg/kg/min) of ULTIVA and 1 mcg/kg IV boluses of ULTIVA. The active control group received 2 mcg/kg IV boluses of fentanyl and increases in placebo IV infusion rate.

The second comparator study, a multi-center, double-blind, randomized, parallel group study (N = 57), compared ULTIVA (n = 35) to fentanyl (n = 22) in adult patients undergoing elective CABG surgery with poor left ventricular function (ejection fraction < 0.35). Subjects received oral lorazepam 40 mcg/kg as premedication. Anesthesia was induced using etomidate until loss of consciousness, followed by a low-dose propofol infusion (3 mg/kg/hr) and pancuronium 0.15 mg/kg. Subjects in the group administered ULTIVA received a placebo bolus dose and a continuous infusion of ULTIVA 1 mcg/kg/min and subjects in the fentanyl group received a bolus loading dose of 15 mcg/kg and placebo continuous infusion. During maintenance, supplemental bolus doses of ULTIVA (0.5 mcg/kg) and infusion rate increases of 0.5 to 1 mcg/kg/min (maximum rate allowed was 4 mcg/kg/min) of ULTIVA were administered to one group; while the fentanyl group was given intermittent maintenance bolus doses of 2 mcg/kg and increases in the placebo infusion rate.

In these two studies, using a high dose opioid technique with ULTIVA as a component of a balanced or total intravenous anesthetic regimen, the remifentanil regimen effectively attenuated response to maximal sternal spread generally better than the dose and regimen studied for the active control (fentanyl). While this provides evidence for the efficacy of remifentanil as an analgesic in this setting, caution must be exercised in interpreting these results as evidence of superiority of remifentanil over the active control, since these studies did not make any attempt to evaluate and compare the optimal analgesic doses of either drug in this setting.

14.6 Neurosurgery

ULTIVA was administered to 61 patients undergoing craniotomy for removal of a supratentorial mass lesion. In these studies, ventilation was controlled to maintain a predicted PaCO2 of approximately 28 mmHg. In one study (n = 30) with ULTIVA and 66% nitrous oxide, the median time to extubation and to patient response to verbal commands was 5 minutes (range -1 to 19 minutes). Intracranial pressure and cerebrovascular responsiveness to carbon dioxide were normal [see Clinical Pharmacology (12.2)].

A randomized, controlled study compared ULTIVA (n = 31) to fentanyl (n = 32). ULTIVA (1 mcg/kg/min) and fentanyl (2 mcg/kg/min) were administered after induction with thiopental and pancuronium. A similar number of patients (6%) receiving ULTIVA and fentanyl had hypotension during induction. Anesthesia was maintained with nitrous oxide and ULTIVA at a mean infusion rate of 0.23 mcg/kg/min (range 0.1 to 0.4) compared with a fentanyl mean infusion rate of 0.04 mcg/kg/min (range 0.02 to 0.07). Supplemental isoflurane was administered as needed. The patients receiving ULTIVA required a lower mean isoflurane dose (0.07 MAC-hours) compared with 0.64 MAC-hours for the fentanyl patients (P = 0.04). ULTIVA was discontinued at the end of anesthesia, whereas fentanyl was discontinued at the time of bone flap replacement (a median time of 44 minutes before the end of surgery). Median time to extubation was similar (5 and 3.5 minutes, respectively, with ULTIVA and fentanyl). None of the patients receiving ULTIVA required naloxone compared to seven of the fentanyl patients (P = 0.01). Eighty-one percent (81%) of patients receiving ULTIVA recovered (awake, alert, and oriented) within 30 minutes after surgery compared with 59% of fentanyl patients (P = 0.06). At 45 minutes, recovery rates were similar (81% and 69% respectively for ULTIVA and fentanyl, P = 0.27). Patients receiving ULTIVA required an analgesic for headache sooner than fentanyl patients (median of 35 minutes compared with 136 minutes, respectively [P = 0.04]). No adverse cerebrovascular effects were seen in this study [see Clinical Pharmacology (12.2)].

14.7 Continuation of Analgesic Use into the Immediate Postoperative Period

Analgesia with ULTIVA in the immediate postoperative period (until approximately 30 minutes after extubation) was studied in 401 patients in four dose-finding studies and in 281 patients in two efficacy studies. In the dose-finding studies, the use of bolus doses of ULTIVA and incremental infusion rate increases ≥ 0.05 mcg/kg/min led to respiratory depression and muscle rigidity.

In two efficacy studies, ULTIVA 0.1 mcg/kg/min was started immediately after discontinuing anesthesia. Incremental infusion rate increases of 0.025 mcg/kg/min every 5 minutes were given to treat moderate to severe postoperative pain. In Study 1, 50% decreases in infusion rate were made if respiratory rate decreased below 12 breaths/min and in Study 2, the same decreases were made if respiratory rate was below 8 breaths/min. With this difference in criteria for infusion rate decrease, the incidence of respiratory depression was lower in Study 1 (4%) than in Study 2 (12%). In both studies, ULTIVA provided effective analgesia (no or mild pain with respiratory rate ≥ 8 breaths/min) in approximately 60% of patients at mean final infusion rates of 0.1 to 0.125 mcg/kg/min.

Study 2 was a double-blind, randomized, controlled study in which patients received either morphine sulfate (0.15 mg/kg administered 20 minutes before the anticipated end of surgery plus 2 mg bolus doses for supplemental analgesia) or ULTIVA (as described above). Emergence from anesthesia was similar between groups; median time to extubation was 5 to 6 minutes for both. ULTIVA provided effective analgesia in 58% of patients compared to 33% of patients who received morphine. Respiratory depression occurred in 12% of patients receiving ULTIVA compared to 4% of morphine patients. For patients who received ULTIVA, morphine sulfate (0.15 mg/kg) was administered in divided doses 5 and 10 minutes before discontinuing ULTIVA. Within 30 minutes after discontinuation of ULTIVA, the percentage of patients with effective analgesia decreased to 34%.

14.8 Monitored Anesthesia Care

ULTIVA has been studied in the monitored anesthesia care setting in 609 patients in eight clinical studies. Nearly all patients received supplemental oxygen in these studies. Two early dose-finding studies demonstrated that use of sedation as an endpoint for titration of ULTIVA led to a high incidence of muscle rigidity (69%) and respiratory depression. Subsequent trials titrated ULTIVA to specific clinical endpoints of patient comfort, analgesia, and adequate respiration (respiratory rate > 8 breaths/min) with a corresponding lower incidence of muscle rigidity (3%) and respiratory depression. With doses of midazolam > 2 mg (4 to 8 mg), the dose of ULTIVA could be decreased by 50%, but the incidence of respiratory depression rose to 32%.

The efficacy of a single dose of ULTIVA (1.0 mcg/kg over 30 seconds) was compared to alfentanil (7 mcg/kg over 30 seconds) in patients undergoing ophthalmic surgery. More patients receiving ULTIVA were pain free at the time of the nerve block (77% versus 44%, P = 0.02) and more experienced nausea (12% versus 4%) than those receiving alfentanil.

In a randomized, controlled study (n = 118), ULTIVA 0.5 mcg/kg over 30 to 60 seconds followed by a continuous infusion of 0.1 mcg/kg/min, was compared to a propofol bolus (500 mcg/kg) followed by a continuous infusion (50 mcg/kg/min) in patients who received a local or regional anesthetic nerve block 5 minutes later. The incidence of moderate or severe pain during placement of the block was similar between groups (2% with ULTIVA and 8% with propofol, P = 0.2) and more patients receiving ULTIVA experienced nausea (26% versus 2%, P < 0.001). The final mean infusion rate of ULTIVA was 0.08 mcg/kg/min.

In a randomized, double-blind study, ULTIVA with or without midazolam was evaluated in 159 patients undergoing superficial surgical procedures under local anesthesia. ULTIVA was administered without midazolam as a 1 mcg/kg dose over 30 seconds followed by a continuous infusion of 0.1 mcg/kg/min. In the group of patients that received midazolam, ULTIVA was administered as a 0.5 mcg/kg dose over 30 seconds followed by a continuous infusion of 0.05 mcg/kg/min and midazolam 2 mg was administered 5 minutes later. The occurrence of moderate or severe pain during the local anesthetic injection was similar between groups (16% and 20%). Other effects for ULTIVA alone and ULTIVA/midazolam were: respiratory depression with oxygen desaturation (SPO2 < 90%), 5% and 2%; nausea, 8% and 2%; and pruritus, 23% and 12%. Titration of ULTIVA resulted in prompt resolution of respiratory depression (median 3 minutes, range 0 to 6 minutes). The final mean infusion rate of ULTIVA was 0.12 mcg/kg/min (range 0.03 to 0.3) for the group receiving ULTIVA alone and 0.07 mcg/kg/min (range 0.02 to 0.2) for the group receiving ULTIVA/midazolam.

16 HOW SUPPLIED/STORAGE AND HANDLING

ULTIVA (remifentanil hydrochloride) for Injection, for intravenous use, is supplied as follows:

NDC Number | Container | Concentration | Quantity
72078-034-01 | 3 mL Single-Dose Vial | 1 mg lyophilized powder | Box of 10
72078-035-02 | 5 mL Single-Dose Vial | 2 mg lyophilized powder | Box of 10
72078-036-05 | 10 mL Single-Dose Vial | 5 mg lyophilized powder | Box of 10

ULTIVA should be stored at 2° to 25°C (36° to 77°F).

Discard unused portion.

17 PATIENT COUNSELING INFORMATION

Addiction, Abuse, and Misuse

Inform patients that the use of ULTIVA, even when taken as recommended, can result in addiction, abuse, and misuse, which can lead to overdose and death [see Warnings and Precautions (5.1)].

Life-Threatening Respiratory Depression

Inform patients of the risk of life-threatening respiratory depression, including information that the risk is greatest when starting ULTIVA or when the dosage is increased, and that it can occur even at recommended dosages.

Hyperalgesia and Allodynia

Advise patients to inform their healthcare provider if they experience symptoms of hyperalgesia, including worsening pain, increased sensitivity to pain, or new pain [see Warnings and Precautions (5.4), Adverse Reactions (6)].

Serotonin Syndrome

Inform patients that opioids could cause a rare but potentially life-threatening condition called serotonin syndrome resulting from concomitant administration of serotonergic drugs. Warn patients of the symptoms of serotonin syndrome and to seek medical attention right away if symptoms develop after discharge from the hospital. Instruct patients to inform their healthcare provider if they are taking, or plan to take serotonergic medications [see Warnings and Precautions (5.5), Drug Interactions (7)].

Constipation

Advise patients of the potential for severe constipation, including management instructions and when to seek medical attention [see Adverse Reactions (6), Clinical Pharmacology (12.2)].

© 202X Viatris Inc.
ULTIVA is a registered trademark of Glaxo Group Limited, a GSK Company, licensed to the Viatris Companies.
Diprivan® is a registered trademark of Fresenius Kabi USA, LLC.

Manufactured for:
Mylan Institutional LLC
Morgantown, WV 26505 U.S.A.

Manufactured by:
Mylan Institutional
Galway, Ireland

XXXXXXXX MI:ULTIIJ:RX11

PRINCIPAL DISPLAY PANEL – 1 mg

NDC 72078-034-01

Ultiva® CII
(remifentanil HCl)
for Injection

1 mg

Equivalent to
1 mg of remifentanil

For Intravenous Use Only

Rx only

10 x 1 mg Single-Dose Vials

Sterile.

Usual Dosage: See accompanying
prescribing information.

Store at 2° to 25°C (36° to 77°F).

To reconstitute solution, add 1 mL of diluent
per mg of remifentanil. Shake well to dissolve.
When reconstituted as directed, the solution
contains approximately 1 mg of remifentanil
activity per 1 mL.

Discard unused portion.

ULTIVA® should be diluted to a
recommended final concentration of 25,
50 or 250 mcg/mL prior to administration.
ULTIVA® should not be administered
without dilution. See package insert.

© 2022 Viatris Inc.

ULTIVA is a registered trademark
of Glaxo Group Limited, a GSK Company,
licensed to the Viatris Companies.

Manufactured for:
Mylan Institutional LLC
Morgantown, WV 26505 U.S.A.

Manufactured by:
Mylan Institutional
Galway, Ireland

MI:034:10C:R1

Mylan.com

PRINCIPAL DISPLAY PANEL – 2 mg

NDC 72078-035-02

Ultiva® CII
(remifentanil HCl)
for Injection

2 mg

Equivalent to
2 mg of remifentanil

For Intravenous Use Only

Rx only

10 x 2 mg Single-Dose Vials

Sterile.

Usual Dosage: See accompanying
prescribing information.

Store at 2° to 25°C (36° to 77°F).

To reconstitute solution, add 1 mL of diluent
per mg of remifentanil. Shake well to dissolve.
When reconstituted as directed, the solution
contains approximately 1 mg of remifentanil
activity per 1 mL.

Discard unused portion.

ULTIVA® should be diluted to a
recommended final concentration of 25,
50 or 250 mcg/mL prior to administration.
ULTIVA® should not be administered
without dilution. See package insert.

© 2022 Viatris Inc.

ULTIVA is a registered trademark
of Glaxo Group Limited, a GSK Company,
licensed to the Viatris Companies.

Manufactured for:
Mylan Institutional LLC
Morgantown, WV 26505 U.S.A.

Manufactured by:
Mylan Institutional
Galway, Ireland

MI:035:10C:R1

Mylan.com

PRINCIPAL DISPLAY PANEL – 5 mg

NDC 72078-036-05

Ultiva® CII
(remifentanil HCl)
for Injection

5 mg

Equivalent to
5 mg of remifentanil

For Intravenous Use Only

Rx only

10 x 5 mg Single-Dose Vials

Sterile.

Usual Dosage: See accompanying
prescribing information.

Store at 2° to 25°C (36° to 77°F).

To reconstitute solution, add 1 mL of diluent
per mg of remifentanil. Shake well to dissolve.
When reconstituted as directed, the solution
contains approximately 1 mg of remifentanil
activity per 1 mL.

Discard unused portion.

ULTIVA® should be diluted to a
recommended final concentration of 25,
50 or 250 mcg/mL prior to administration.
ULTIVA® should not be administered
without dilution. See package insert.

© 2022 Viatris Inc.

ULTIVA is a registered trademark
of Glaxo Group Limited, a GSK Company,
licensed to the Viatris Companies.

Manufactured for:
Mylan Institutional LLC
Morgantown, WV 26505 U.S.A.

Manufactured by:
Mylan Institutional
Galway, Ireland

MI:036:10C:R1

Mylan.com